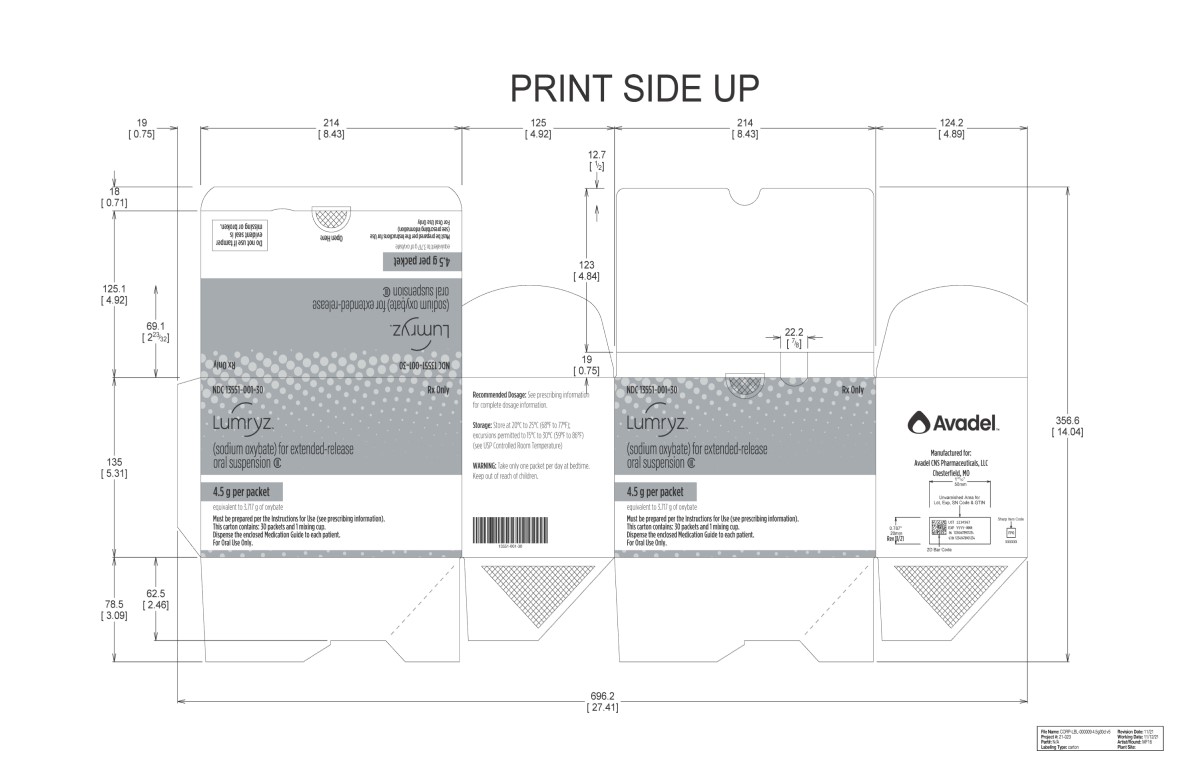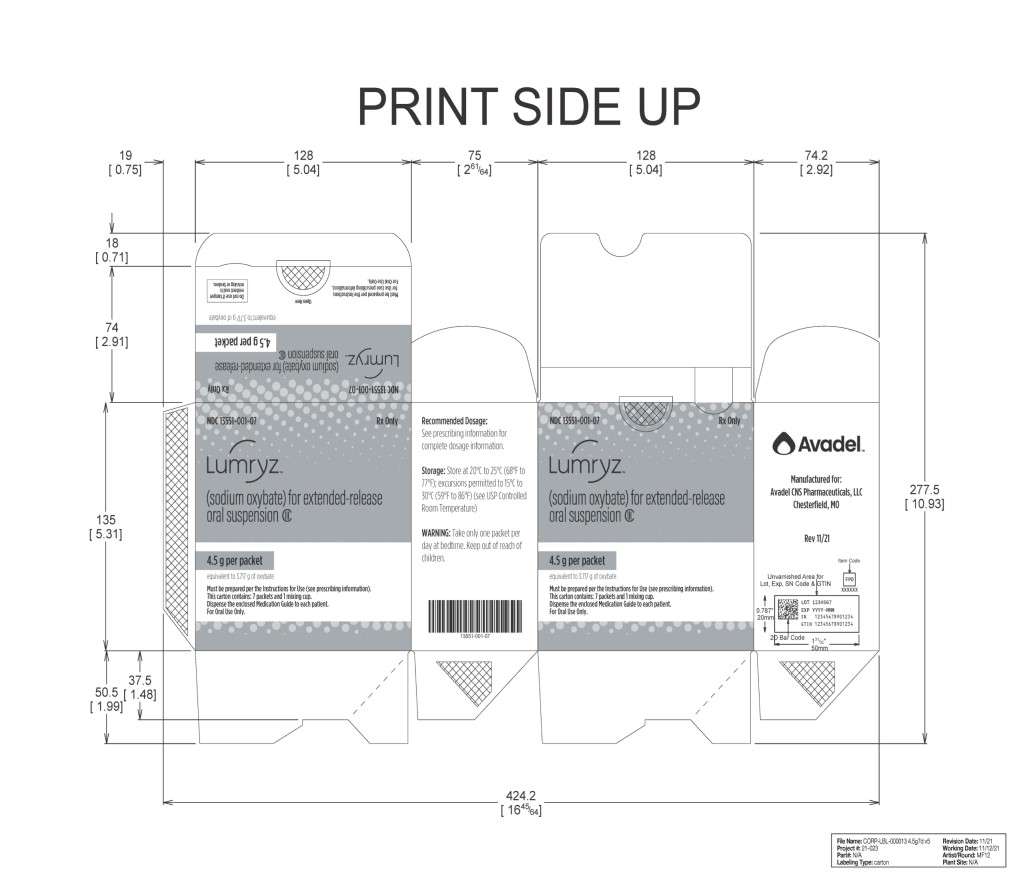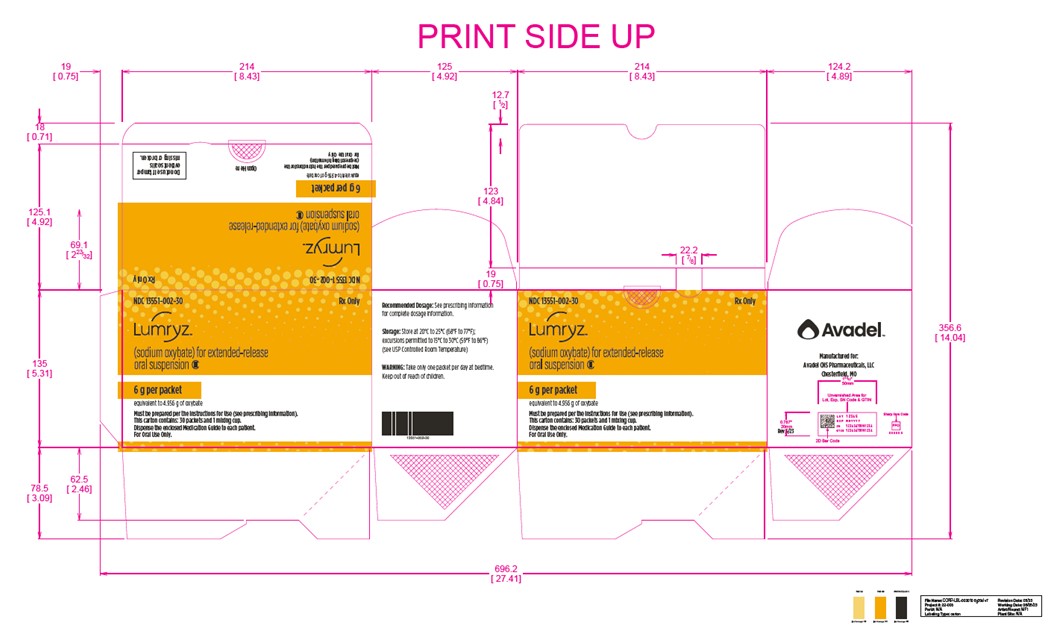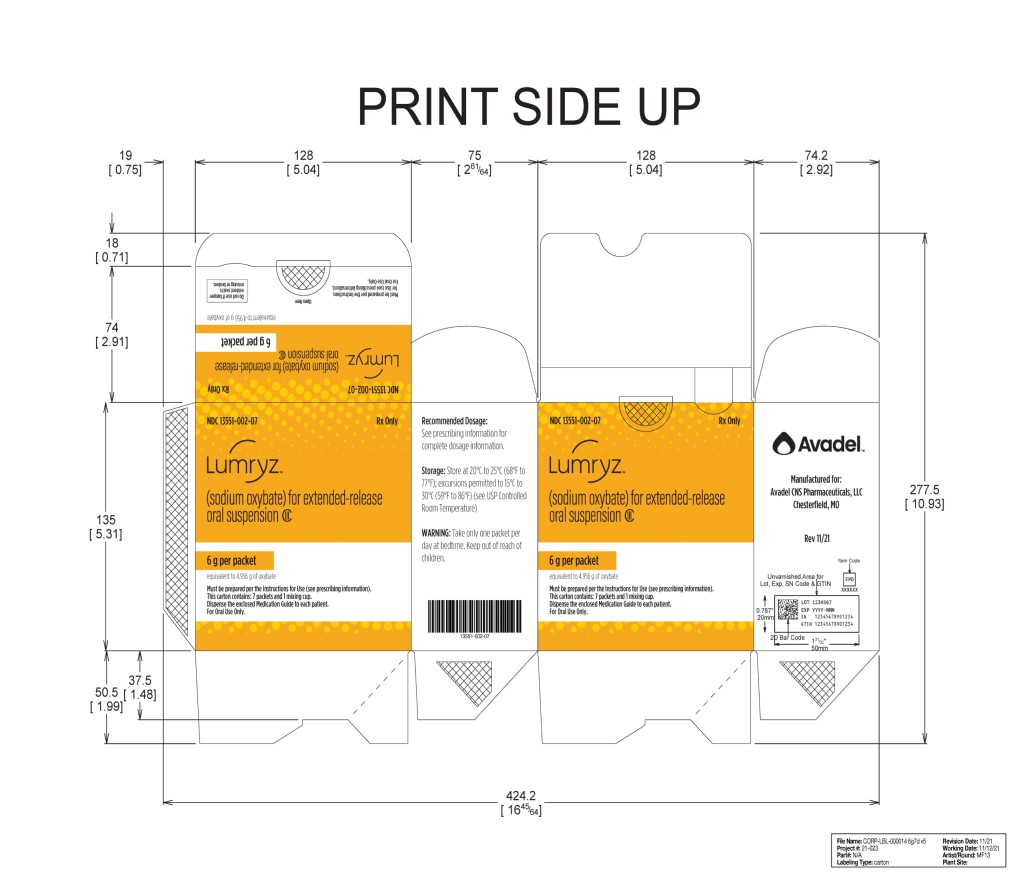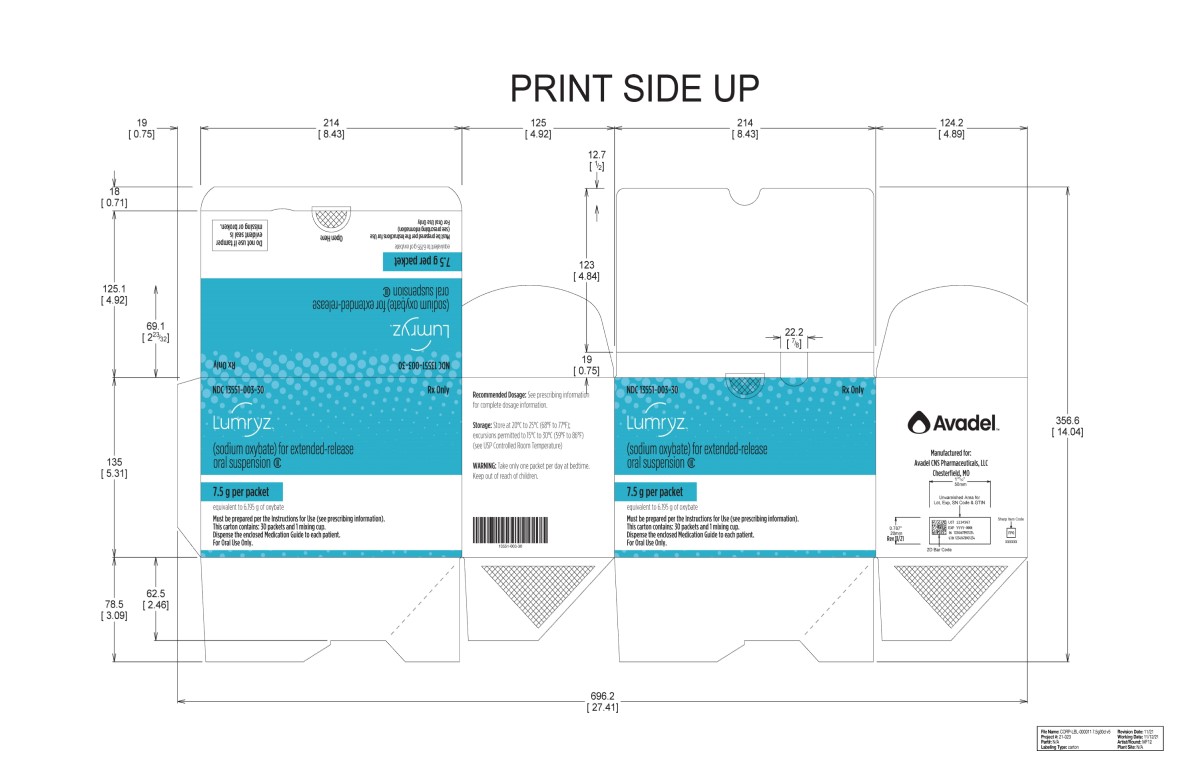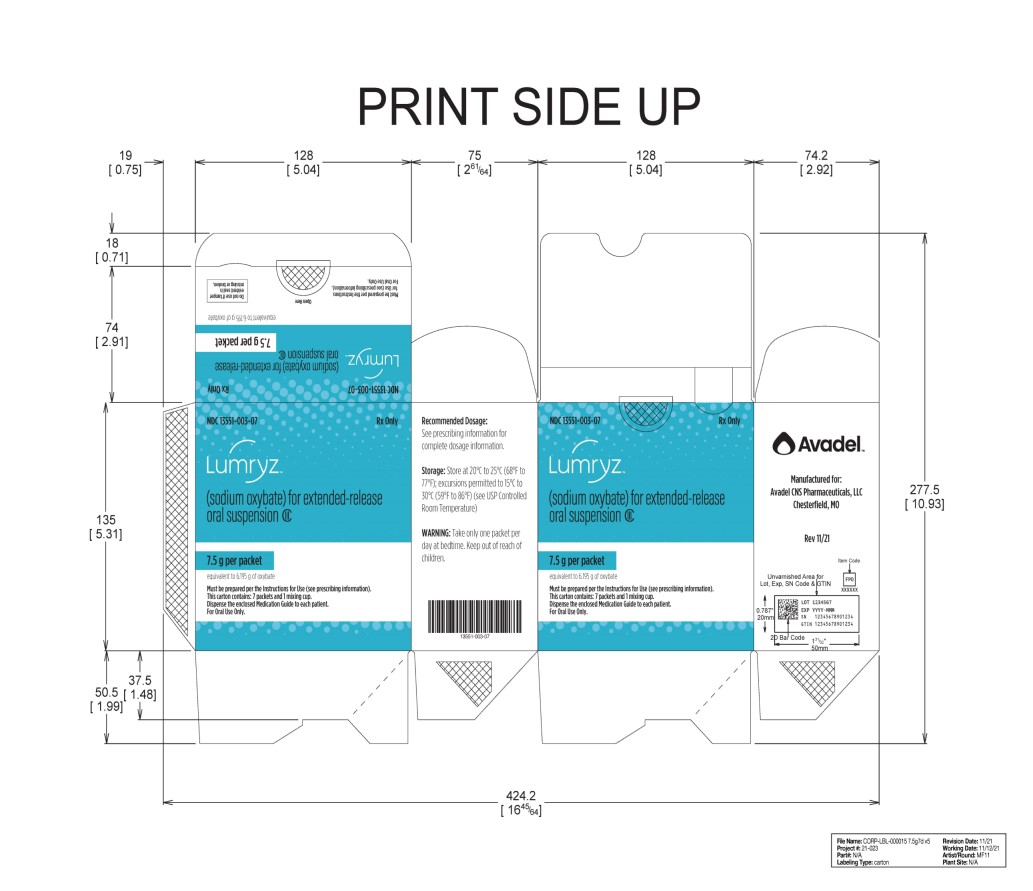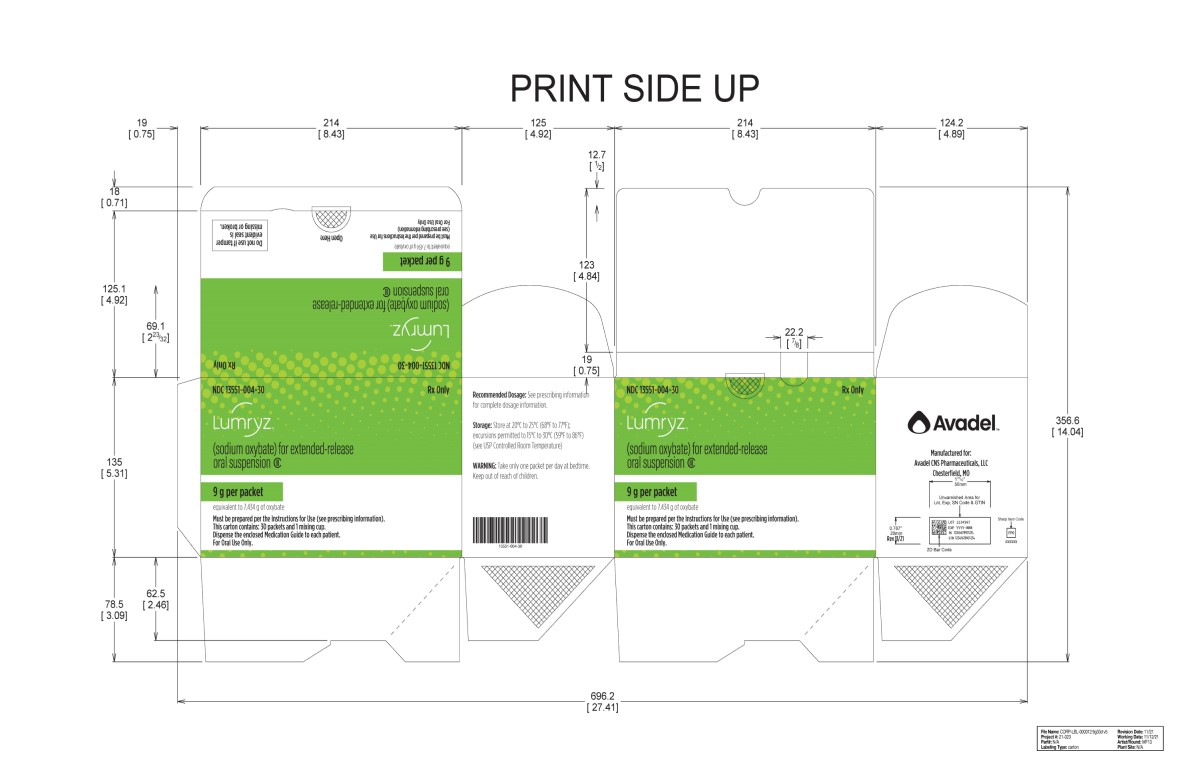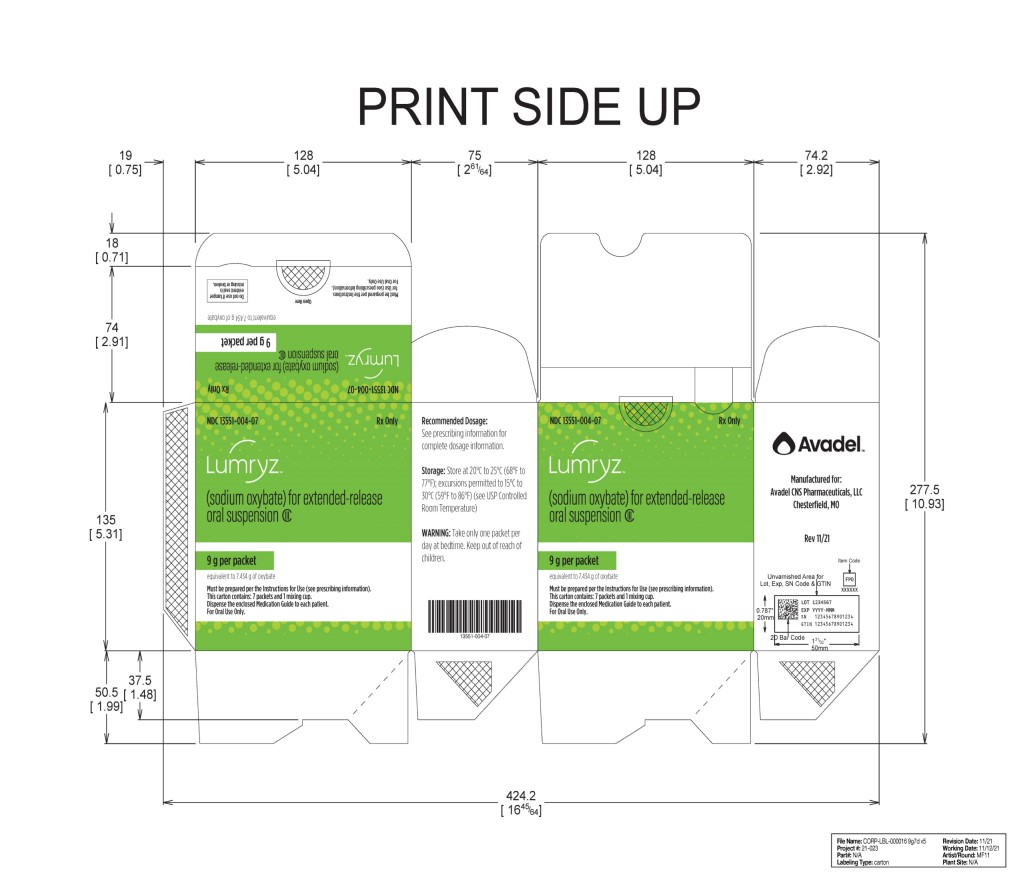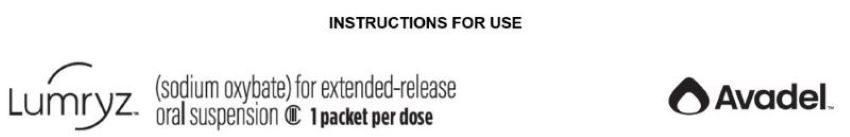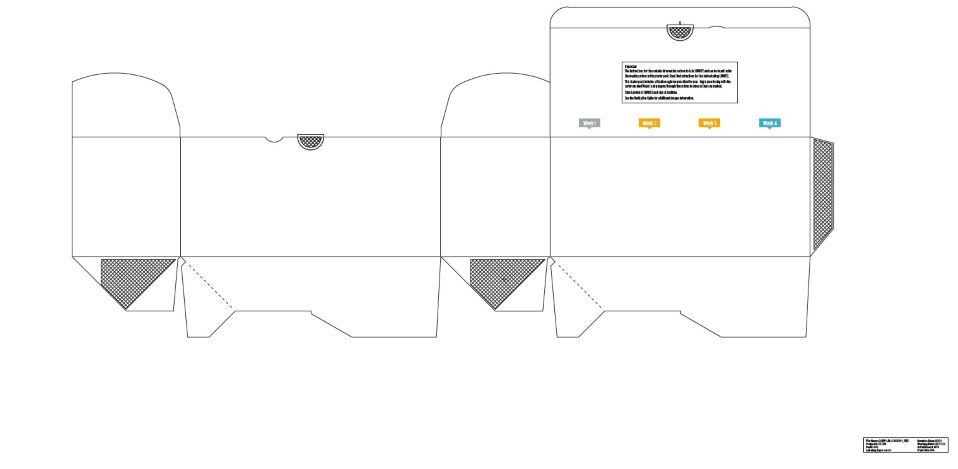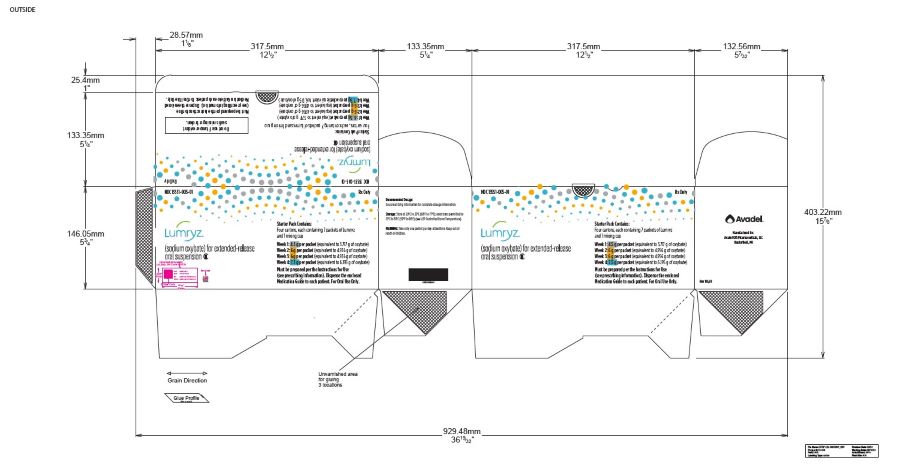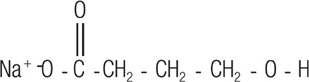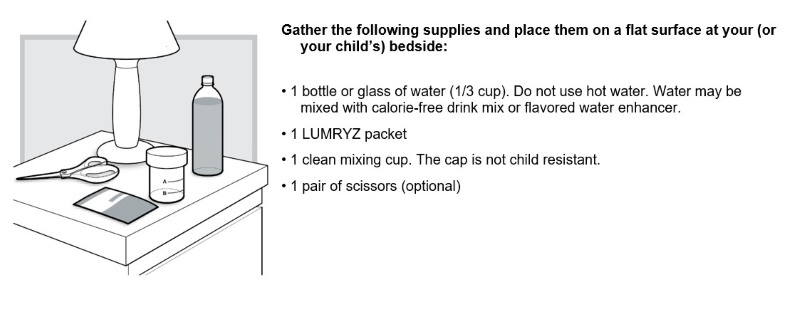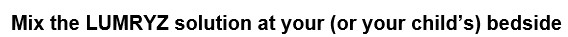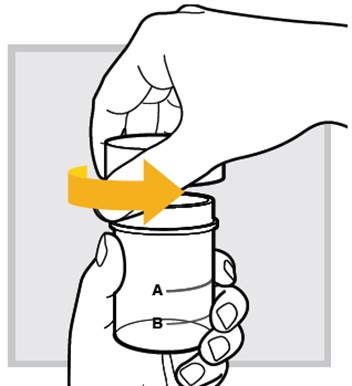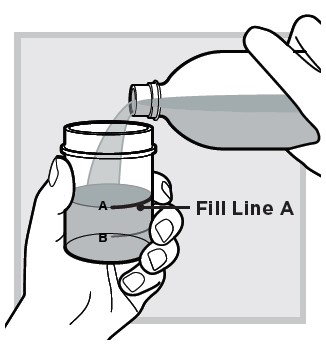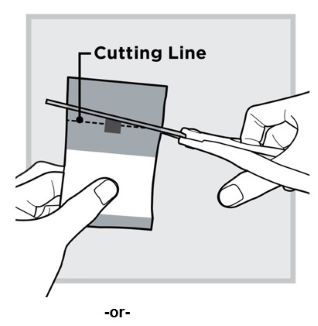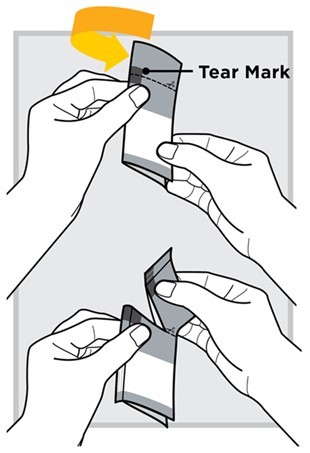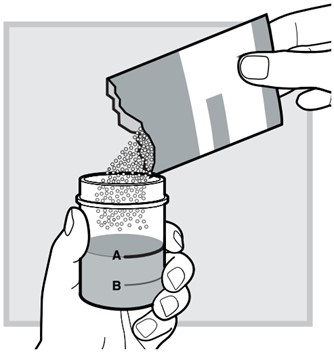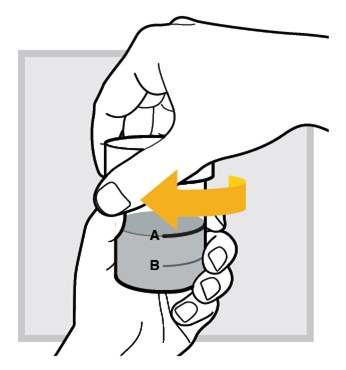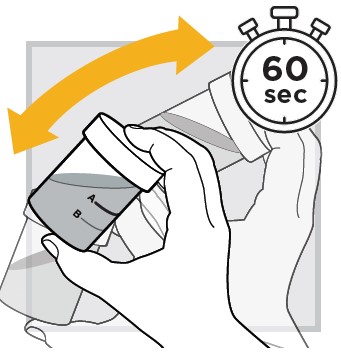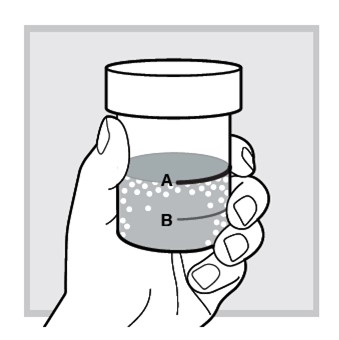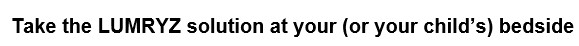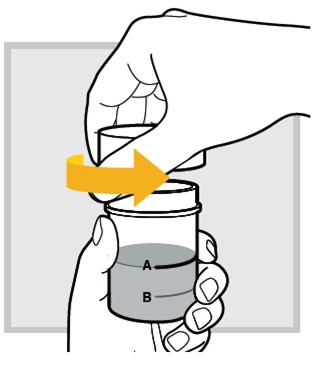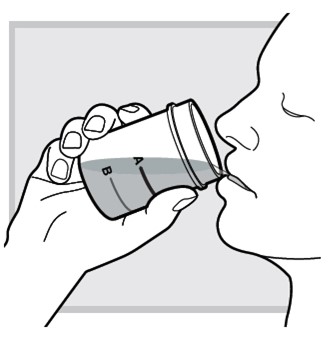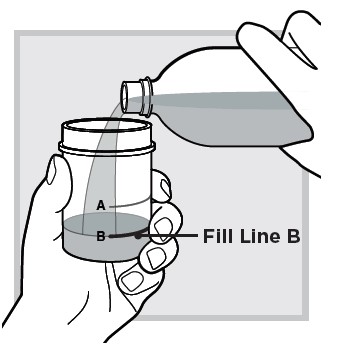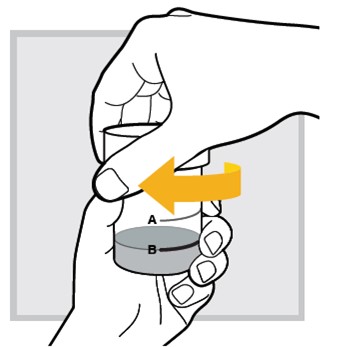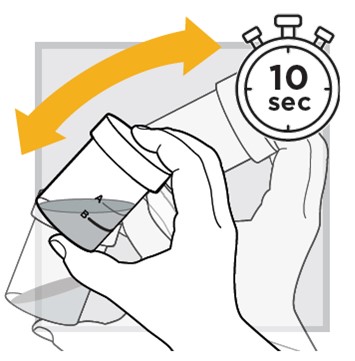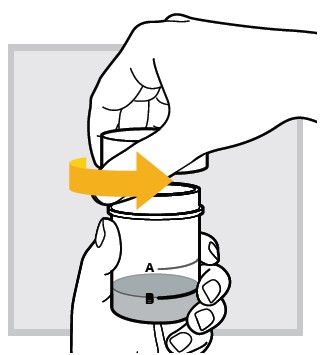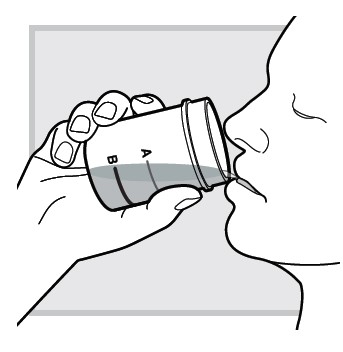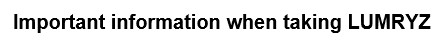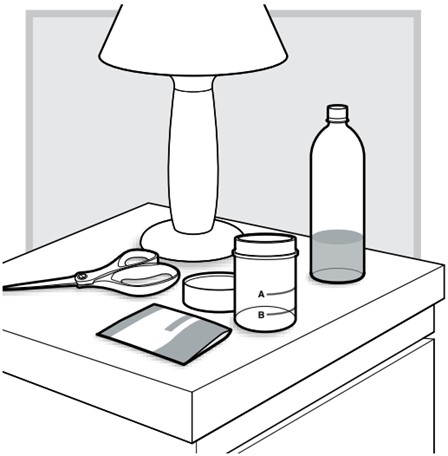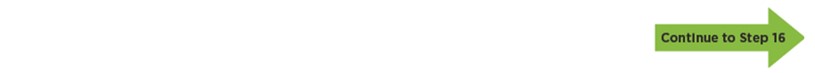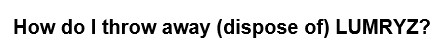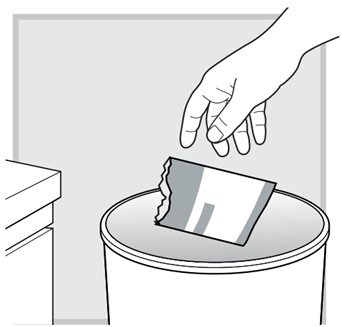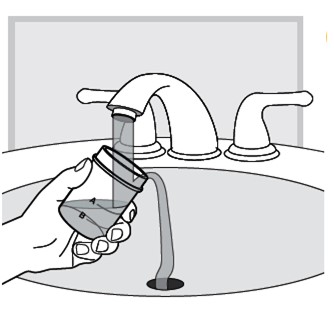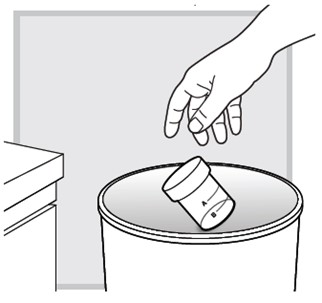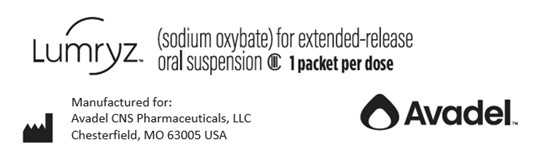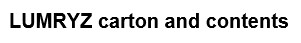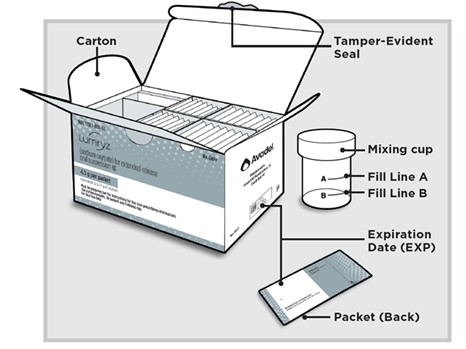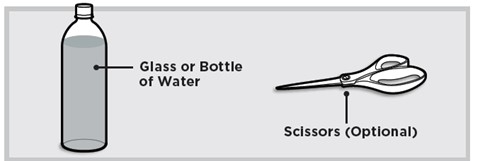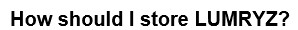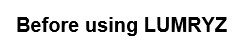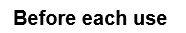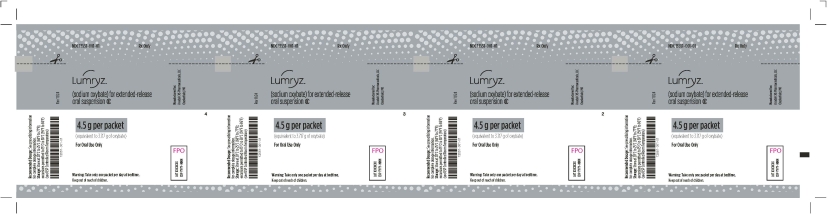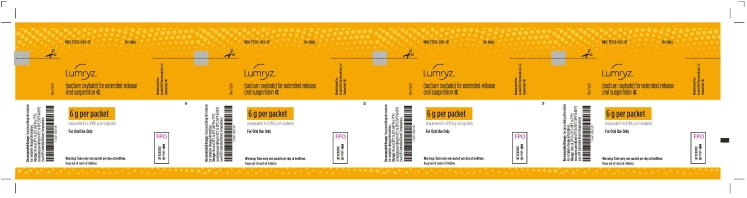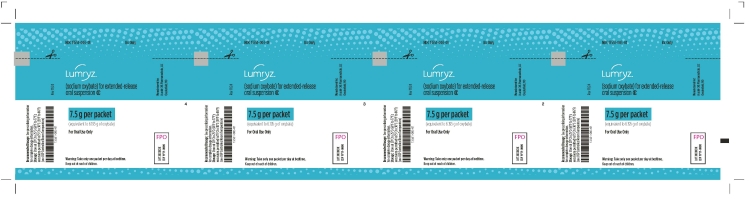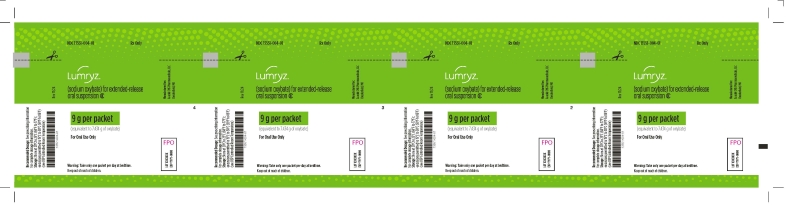 DRUG LABEL: Lumryz
NDC: 13551-001 | Form: FOR SUSPENSION, EXTENDED RELEASE
Manufacturer: Avadel CNS Pharmaceuticals, LLC
Category: prescription | Type: HUMAN PRESCRIPTION DRUG LABEL
Date: 20251204
DEA Schedule: CIII

ACTIVE INGREDIENTS: SODIUM OXYBATE 4.5 g/1 1

HIGHLIGHTS OF PRESCRIBING INFORMATION

These highlights do not include all the information needed to use LUMRYZ™ safely and effectively. See full prescribing information for LUMRYZ.
LUMRYZ (sodium oxybate) for extended-release oral suspension, CIII
Initial U.S. Approval: 2002

WARNING: CENTRAL NERVOUS SYSTEM (CNS) DEPRESSION AND ABUSE AND MISUSE

See full prescribing information for complete boxed warning.

Central Nervous System Depression

• LUMRYZ is a CNS depressant, and respiratory depression can occur with LUMRYZ use (5.1, 5.4)

Abuse and Misuse

• LUMRYZ is the sodium salt of gamma-hydroxybutyrate (GHB). Abuse or misuse of illicit GHB is associated with CNS adverse reactions, including seizure, respiratory depression, decreased consciousness, coma, and death (5.2, 9.2)

LUMRYZ is available only through a restricted program called the LUMRYZ REMS (5.3)

RECENT MAJOR CHANGES

Dosage and Administration (2.3) 11/2025

1 INDICATIONS AND USAGE

LUMRYZ is a central nervous system depressant indicated for the treatment of cataplexy or excessive daytime sleepiness (EDS) in patients 7 years of age and older with narcolepsy (1).

2 DOSAGE AND ADMINISTRATION

Dosing for Adults:

• Initiate dosage at 4.5 g once per night orally (2.1).

• Titrate to effect in increments of 1.5 g per night at weekly intervals (2.1).

• Recommended dosage range: 6 g to 9 g once per night orally (2.1).

Dosing for Pediatric Patients (7 Years of Age and Older):

• The recommended starting dosage, titration regimen, and maximum total nightly dosage are based on body weight (2.2)

• Pediatric patients 7 years and older weighing at least 45 kg: The recommended starting dosage is 4.5 g once per night. Increase the dosage by 1.5 g per night at weekly intervals to the maximum recommended dosage of 9 g once per night orally. The dosage may be gradually titrated based on efficacy and tolerability (2.2).

• Pediatric patients 7 years and older weighing less than 45 kg: Because the recommended starting dosage cannot be achieved with the available strengths of LUMRYZ, use another sodium oxybate product to initiate treatment (2.2).

Important Administration Information

• Prepare the dose of LUMRYZ prior to bedtime; suspend dose in approximately ⅓ cup of water (with or without calorie-free drink mix or flavored water enhancer) in the mixing cup provided (2.3).

• Allow 2 hours after eating before dosing (2.3).

• Take LUMRYZ while in bed and lie down after dosing (2.3).

3 DOSAGE FORMS AND STRENGTHS

For extended-release oral suspension: Packets of 4.5 g, 6 g, 7.5 g, or 9 g (3)

4 CONTRAINDICATIONS

• In combination with sedative hypnotics or alcohol (4).

• Succinic semialdehyde dehydrogenase deficiency (4).

5 WARNINGS AND PRECAUTIONS

• CNS depression: Use caution when considering the concurrent use of LUMRYZ with other CNS depressants (5.1).

• Caution patients against hazardous activities requiring complete mental alertness or motor coordination within the first 6 hours of dosing or after first initiating treatment until certain that LUMRYZ does not affect them adversely (5.1).

• Depression and suicidality: Monitor patients for emergent or increased depression and suicidality (5.5).

• Confusion/Anxiety: Monitor for impaired motor/cognitive function (5.6).

• Parasomnias: Evaluate episodes of sleepwalking (5.7).

• High sodium content in LUMRYZ: Monitor patients with heart failure, hypertension, or impaired renal function (5.8).

6 ADVERSE REACTIONS

Most common adverse reactions in adults (incidence ≥ 5% and greater than placebo) reported for any dose of LUMRYZ were nausea, dizziness, enuresis, headache, and vomiting (6.1).

Most common adverse reactions for pediatric patients (≥ 5%) in a study with immediate-release sodium oxybate were nausea, enuresis, vomiting, headache, weight decreased, decreased appetite, dizziness, and sleepwalking (6.1).

To report SUSPECTED ADVERSE REACTIONS, contact Avadel CNS Pharmaceuticals, LLC at 1-888-828-2335 or FDA at 1-800-FDA-1088 or www.fda.gov/medwatch.

8 USE IN SPECIFIC POPULATIONS

• Pregnancy: Based on animal data, may cause fetal harm (8.1).

• Geriatric patients: Monitor for impaired motor and/or cognitive function when taking LUMRYZ (8.5).

• Hepatic Impairment: Because of an increase in exposure, LUMRYZ should not be initiated in patients with hepatic impairment because appropriate dosage adjustments for initiation of LUMRYZ cannot be made (8.6).

FULL PRESCRIBING INFORMATION

WARNING: CENTRAL NERVOUS SYSTEM (CNS) DEPRESSION AND ABUSE AND MISUSE

Central Nervous System Depression

LUMRYZ (sodium oxybate) is a CNS depressant. Clinically significant respiratory depression and obtundation may occur in patients treated with LUMRYZ at recommended doses [see Warnings and Precautions (5.1)]. Many patients who received sodium oxybate during clinical trials in narcolepsy were receiving central nervous system stimulants [see Clinical Trials (14)].

Abuse and Misuse

LUMRYZ (sodium oxybate) is the sodium salt of gamma-hydroxybutyrate (GHB). Abuse or misuse of illicit GHB, either alone or in combination with other CNS depressants, is associated with CNS adverse reactions, including seizure, respiratory depression, decreases in the level of consciousness, coma, and death [see Warnings and Precautions (5.2)].

Because of the risks of CNS depression and abuse and misuse, LUMRYZ is available only through a restricted program under a Risk Evaluation and Mitigation Strategy (REMS) called the LUMRYZ REMS [see Warnings and Precautions (5.3)].

1 INDICATIONS AND USAGE

LUMRYZ is indicated for the treatment of cataplexy or excessive daytime sleepiness (EDS) in patients 7 years of age and older with narcolepsy.

2 DOSAGE AND ADMINISTRATION

2.1 Adult Dosing Information

The recommended starting dosage of LUMRYZ in adults is 4.5 grams (g) once per night administered orally. Increase the dosage by 1.5 g per night at weekly intervals to the recommended dosage range of 6 g to 9 g once per night orally. The dosage may be gradually titrated based on efficacy and tolerability. Doses higher than 9 g per night have not been studied and should not ordinarily be administered.

2.2 Pediatric Dosing Information

The recommended starting pediatric dosage, titration regimen, and maximum total nightly dosage are based on patient weight.

Pediatric Patients 7 years and Older Weighing at least 45 kg

The recommended starting dosage of LUMRYZ in pediatric patients 7 years and older weighing at least 45 kg is 4.5 g once per night administered orally. Increase the dosage by 1.5 g per night at weekly intervals to the maximum recommended dosage of 9 g once per night orally. The dosage may be gradually titrated based on efficacy and tolerability.

Pediatric Patients 7 years and Older Weighing Less than 45 kg

Because the recommended starting dosage in pediatric patients 7 years and older weighing less than 45 kg cannot be achieved with the available strengths of LUMRYZ, use another sodium oxybate product to initiate treatment. Refer to the Prescribing Information of other sodium oxybate products for the recommended dosage for those products.

The maximum recommended dosage for patients 7 years and older weighing 20 kg to <30 kg is 6 g once per night orally, and the maximum recommended dosage for patients 7 years and older weighing 30 kg to <45 kg is 7.5 g once per night orally [see Dosage and Administration (2.4)]. There is insufficient information to provide specific dosing recommendations for patients 7 years and older who weigh less than 20 kg.

2.3 Important Administration Instructions

LUMRYZ is taken orally as a single dose at bedtime. Prepare the dose of LUMRYZ prior to bedtime. Prior to ingestion, the dose of LUMRYZ should be suspended in approximately 1/3 cup (approximately 80 mL) of water (with or without calorie-free drink mix or flavored water enhancer) in the mixing cup provided [see Instructions for Use]. Do not use hot water [see Clinical Pharmacology (12.3)]. After mixing, consume LUMRYZ within 30 minutes.

Take LUMRYZ at least 2 hours after eating [see Clinical Pharmacology (12.3)].

Patients should take LUMRYZ while in bed and lie down immediately after dosing as LUMRYZ may cause them to fall asleep abruptly without first feeling drowsy. Patients will often fall asleep within 5 minutes of taking LUMRYZ, and will usually fall asleep within 15 minutes, though the time it takes any individual patient to fall asleep may vary from night to night. Patients should remain in bed following ingestion of LUMRYZ.

2.4 Switching Patients from Immediate-Release Sodium Oxybate

Patients who are currently being treated with immediate-release sodium oxybate may be switched to LUMRYZ at the nearest equivalent dosage in grams per night (e.g., 7.5 g sodium oxybate divided into two 3.75 g doses per night to 7.5 g LUMRYZ once per night).

3 DOSAGE FORMS AND STRENGTHS

For extended-release oral suspension: LUMRYZ is a white to off-white powder provided in packets of 4.5 g, 6 g, 7.5 g, or 9 g of sodium oxybate.

4 CONTRAINDICATIONS

LUMRYZ is contraindicated for use in:

● combination with sedative hypnotics [see Warnings and Precautions (5.1)]

● combination with alcohol [see Warnings and Precautions (5.1)]

● patients with succinic semialdehyde dehydrogenase deficiency [see Clinical Pharmacology (12.3)]

5 WARNINGS AND PRECAUTIONS

5.1 Central Nervous System Depression

LUMRYZ is a central nervous system (CNS) depressant. Clinically significant respiratory depression and obtundation has occurred in patients treated with immediate-release sodium oxybate at recommended doses in clinical trials and may occur in patients treated with LUMRYZ at recommended doses. LUMRYZ is contraindicated in combination with alcohol and sedative hypnotics. The concurrent use of LUMRYZ with other CNS depressants, including but not limited to opioid analgesics, benzodiazepines, sedating antidepressants or antipsychotics, sedating antiepileptic drugs, general anesthetics, muscle relaxants, and/or illicit CNS depressants, may increase the risk of respiratory depression, hypotension, profound sedation, syncope, and death. If use of these CNS depressants in combination with LUMRYZ is required, dose reduction or discontinuation of one or more CNS depressants (including LUMRYZ) should be considered. In addition, if short-term use of an opioid (e.g., post- or perioperative) is required, interruption of treatment with LUMRYZ should be considered. In addition to coadministration of LUMRYZ and alcohol being contraindicated because of respiratory depression, consumption of alcohol while taking LUMRYZ may also result in a more rapid release of the dose of sodium oxybate [see Clinical Pharmacology (12.3)].

Healthcare providers should caution patients about operating hazardous machinery, including automobiles or airplanes, until they are reasonably certain that LUMRYZ does not affect them adversely (e.g., impair judgment, thinking, or motor skills). Patients should not engage in hazardous occupations or activities requiring complete mental alertness or motor coordination, such as operating machinery or a motor vehicle or flying an airplane, for at least 6 hours after taking LUMRYZ. Patients should be queried about CNS depression-related events upon initiation of LUMRYZ therapy and periodically thereafter.

LUMRYZ is available only through a restricted program under a REMS [see Warnings and Precautions (5.3)].

5.2 Abuse and Misuse

LUMRYZ is a Schedule III controlled substance. The active ingredient of LUMRYZ, sodium oxybate, is the sodium salt of gamma-hydroxybutyrate (GHB), a Schedule I controlled substance. Abuse of illicit GHB, either alone or in combination with other CNS depressants, is associated with CNS adverse reactions, including seizure, respiratory depression, decreases in the level of consciousness, coma, and death. The rapid onset of sedation, coupled with the amnestic features of GHB, particularly when combined with alcohol, has proven to be dangerous for the voluntary and involuntary user (e.g., assault victim). Because illicit use and abuse of GHB have been reported, physicians should carefully evaluate patients for a history of drug abuse and follow such patients closely, observing them for signs of misuse or abuse of GHB (e.g., increase in size or frequency of dosing, drug-seeking behavior, feigned cataplexy) [see Warnings and Precautions (5.3) and Drug Abuse and Dependence (9.2)].

LUMRYZ is available only through a restricted program under a REMS [see Warnings and Precautions (5.3)].

5.3 LUMRYZ REMS

LUMRYZ is available only through a restricted distribution program called the LUMRYZ REMS because of the risks of central nervous system depression and abuse and misuse [see Warnings and Precautions (5.1, 5.2)].

Notable requirements of the LUMRYZ REMS include the following:

● Healthcare providers who prescribe LUMRYZ are specially certified.

● LUMRYZ will be dispensed only by pharmacies that are specially certified.

● LUMRYZ will be dispensed and shipped only to patients who are enrolled in the LUMRYZ REMS with documentation of safe use conditions.

Further information is available at www.LUMRYZREMS.com or by calling 1-877-453-1029.

5.4 Respiratory Depression and Sleep-Disordered Breathing

LUMRYZ may impair respiratory drive, especially in patients with compromised respiratory function. In overdoses of oxybate and with illicit use of GHB, life-threatening respiratory depression has been reported [see Overdosage (10)].

Increased apnea and reduced oxygenation may occur with LUMRYZ administration. A significant increase in the number of central apneas and clinically significant oxygen desaturation may occur in patients with obstructive sleep apnea treated with LUMRYZ.

During polysomnographic evaluation (PSG), central sleep apnea and oxygen desaturation were observed in pediatric patients with narcolepsy treated with immediate-release sodium oxybate.

In adult clinical trials of LUMRYZ in patients with narcolepsy, no subjects with apnea/hypopnea indexes greater than 15 were allowed to enroll.

In an adult study assessing the respiratory-depressant effects of immediate-release sodium oxybate at doses up to 9 g per night in 21 patients with narcolepsy, no dose-related changes in oxygen saturation were demonstrated in the group as a whole. One of four patients with preexisting moderate-to-severe sleep apnea had significant worsening of the apnea/hypopnea index during treatment.

In an adult study assessing the effects of immediate-release sodium oxybate 9 g per night in 50 patients with obstructive sleep apnea, immediate-release sodium oxybate did not increase the severity of sleep-disordered breathing and did not adversely affect the average duration and severity of oxygen desaturation overall. However, there was a significant increase in the number of central apneas in patients taking immediate-release sodium oxybate, and clinically significant oxygen desaturation (≤55%) was measured in three patients (6%) after administration, with one patient withdrawing from the study and two continuing after single brief instances of desaturation.

In adult clinical trials in 128 patients with narcolepsy administered immediate-release sodium oxybate, two subjects had profound CNS depression, which resolved after supportive respiratory intervention. Two other patients discontinued immediate-release sodium oxybate because of severe difficulty breathing and an increase in obstructive sleep apnea. In two controlled trials assessing polysomnographic (PSG) measures in adult patients with narcolepsy administered immediate-release sodium oxybate, 40 of 477 patients were included with a baseline apnea/hypopnea index of 16 to 67 events per hour, indicative of mild to severe sleep-disordered breathing. None of the 40 patients had a clinically significant worsening of respiratory function, as measured by apnea/hypopnea index and pulse oximetry at doses of 4.5 g to 9 g per night.

Prescribers should be aware that sleep-related breathing disorders tend to be more prevalent in obese patients, in men, in postmenopausal women not on hormone replacement therapy, and among patients with narcolepsy. Increased central apneas and clinically relevant desaturation events have been observed with immediate-release sodium oxybate administration in adult and pediatric patients.

5.5 Depression and Suicidality

Depression, and suicidal ideation and behavior, can occur in patients treated with LUMRYZ.

In an adult clinical trial in patients with narcolepsy administered LUMRYZ [see Adverse Reactions (6.1)], there were no suicide attempts, but one patient developed suicidal ideation at the 9 g dose. In adult clinical trials in patients with narcolepsy (n=781) administered immediate-release sodium oxybate, there were two suicides and two attempted suicides in patients treated with immediate-release sodium oxybate, including three patients with a previous history of depressive psychiatric disorder. Of the two suicides, one patient used immediate-release sodium oxybate in conjunction with other drugs. Immediate-release sodium oxybate was not involved in the second suicide. Adverse reactions of depression were reported by 7% of 781 patients treated with immediate-release sodium oxybate, with four patients (<1%) discontinuing because of depression. In most cases, no change in immediate-release sodium oxybate treatment was required.

In a controlled trial in adults with narcolepsy administered LUMRYZ where patients were titrated from 4.5 g to 9 g per night, the incidences of depression were 0% at 4.5 g, 1% at 6 g, 1.1% at 7.5 g, and 1.3% at 9 g. In a controlled adult trial, with patients randomized to fixed doses of 3 g, 6 g, or 9 g per night immediate-release sodium oxybate or placebo, there was a single event of depression at the 3 g per night dose. In another adult controlled trial, with patients titrated from an initial 4.5 g per night starting dose of immediate-release sodium oxybate, the incidences of depression were 1.7%, 1.5%, 3.2%, and 3.6% for the placebo, 4.5 g, 6 g, and 9 g per night doses, respectively.

In a clinical trial in pediatric patients with narcolepsy (n=104) administered immediate-release sodium oxybate, one patient experienced suicidal ideation and two patients reported depression while taking immediate-release sodium oxybate.

The emergence of depression in patients treated with LUMRYZ requires careful and immediate evaluation. Patients with a previous history of a depressive illness and/or suicide attempt should be monitored carefully for the emergence of depressive symptoms while taking LUMRYZ.

5.6 Other Behavioral or Psychiatric Adverse Reactions

Other behavioral and psychiatric adverse reactions can occur in patients taking LUMRYZ.

During adult clinical trials in patients with narcolepsy administered LUMRYZ, 2% of 107 patients treated with LUMRYZ experienced a confusional state. During adult clinical trials in patients with narcolepsy administered immediate-release sodium oxybate, 3% of 781 patients treated with immediate-release sodium oxybate experienced confusion, with incidence generally increasing with dose.

No patients treated with LUMRYZ discontinued treatment because of confusion. Less than 1% of patients discontinued the immediate-release sodium oxybate because of confusion. Confusion was reported at all recommended doses of immediate-release sodium oxybate from 6 g to 9 g per night. In a controlled trial in adults where patients were randomized to immediate-release sodium oxybate in fixed total daily doses of 3 g, 6 g, or 9 g per night or placebo, a dose-response relationship for confusion was demonstrated, with 17% of patients at 9 g per night experiencing confusion. In that controlled trial, the confusion resolved in all cases soon after termination of treatment. In one trial where immediate-release sodium oxybate was titrated from an initial 4.5 g per night dose, there was a single event of confusion in one patient at the 9 g per night dose. In the majority of cases in all adult clinical trials in patients with narcolepsy administered immediate-release sodium oxybate, confusion resolved either soon after termination of dosing or with continued treatment.

Anxiety occurred in 7.5% of 107 patients treated with LUMRYZ in the adult trial in patients with narcolepsy. Anxiety occurred in 5.8% of the 874 patients receiving immediate-release sodium oxybate in adult clinical trials in another population.

Other psychiatric reactions reported in adult clinical trials in patients with narcolepsy administered LUMRYZ included irritability, emotional disorder, panic attack, agitation, delirium, and obsessive thoughts. Other neuropsychiatric reactions reported in adult clinical trials in patients with narcolepsy administered immediate-release sodium oxybate and in the postmarketing setting for immediate-release sodium oxybate include hallucinations, paranoia, psychosis, aggression, and agitation.

In a clinical trial in pediatric patients with narcolepsy administered immediate-release sodium oxybate, neuropsychiatric reactions, including acute psychosis, confusion, and anxiety were reported while taking immediate-release sodium oxybate.

The emergence or increase in the occurrence of behavioral or psychiatric events in patients taking LUMRYZ should be carefully monitored.

5.7 Parasomnias

Parasomnias can occur in patients taking LUMRYZ.

Sleepwalking, defined as confused behavior occurring at night and at times associated with wandering, was reported in 3% of 107 adult patients with narcolepsy treated with LUMRYZ. No patients treated with LUMRYZ discontinued due to sleepwalking. Sleepwalking was reported in 6% of 781 patients with narcolepsy treated with immediate-release sodium oxybate in adult controlled and long-term open-label studies, with <1% of patients discontinuing due to sleepwalking. In controlled trials, rates of sleepwalking were similar for patients taking placebo and patients taking immediate-release sodium oxybate. It is unclear if some or all of the reported sleepwalking episodes correspond to true somnambulism, which is a parasomnia occurring during non-REM sleep, or to any other specific medical disorder. Five instances of sleepwalking with potential injury or significant injury were reported during a clinical trial of immediate-release sodium oxybate in patients with narcolepsy.

Parasomnias, including sleepwalking, have been reported in a pediatric clinical trial and in postmarketing experience with immediate-release sodium oxybate. Therefore, episodes of sleepwalking should be fully evaluated, and appropriate interventions considered.

5.8 Use in Patients Sensitive to High Sodium Intake

LUMRYZ has a high sodium content. In patients sensitive to sodium intake (e.g., those with heart failure, hypertension, or renal impairment), consider the amount of daily sodium intake in each dose of LUMRYZ. Table 1 provides the approximate sodium content per LUMRYZ dose.

Table 1: Approximate Sodium Content per Total Nightly Dose of LUMRYZ (g = grams)
LUMRYZ Dose | Sodium Content/Total Nightly Exposure
4.5 g per night | 820 mg
6 g per night | 1100 mg
7.5 g per night | 1400 mg
9 g per night | 1640 mg

6 ADVERSE REACTIONS

The following clinically significant adverse reactions appear in other sections of the labeling:

● CNS Depression [see Warnings and Precautions (5.1)]

● Abuse and Misuse [see Warnings and Precautions (5.2)]

● Respiratory Depression and Sleep-Disordered Breathing [see Warnings and Precautions (5.4)]

● Depression and Suicidality [see Warnings and Precautions (5.5)]

● Other Behavioral or Psychiatric Adverse Reactions [see Warnings and Precautions (5.6)]

● Parasomnias [see Warnings and Precautions (5.7)]

● Use in Patients Sensitive to High Sodium Intake [see Warnings and Precautions (5.8)]

6.1 Clinical Trials Experience

Because clinical trials are conducted under widely varying conditions, adverse reaction rates observed in the clinical trials of a drug cannot be directly compared to rates in the clinical trials of another drug and may not reflect the rates observed in clinical practice.

Adult Patients

LUMRYZ was studied in one placebo-controlled trial (Study 1) [see Clinical Studies (14.1)] in 212 patients with narcolepsy (107 patients treated with LUMRYZ and 105 with placebo).

Adverse Reactions Leading to Treatment Discontinuation

In Study 1, 15.9% of patients treated with LUMRYZ discontinued because of adverse reactions, compared to 1.9% of patients receiving placebo. The most common adverse reaction leading to discontinuation was dizziness (4.7%). For LUMRYZ, 5.6% of patients discontinued due to adverse reactions on 4.5 g, 4.1% on 6 g, 4.5% on 7.5 g, and 3.9% on 9 g dose.

Most Common Adverse Reactions

The most common adverse reactions (incidence ≥5% and greater than placebo) reported for any dose of LUMRYZ were nausea, dizziness, enuresis, headache, and vomiting.

Adverse Reactions Occurring at an Incidence of 2% or Greater

Table 2 lists adverse reactions occurring in 2% or more of LUMRYZ-treated patients on any individual dose and at a rate greater than placebo-treated patients in Study 1.

Table 2: Adverse Reactions Occurring in 2% or More of LUMRYZ-Treated Adult Patients and Greater than for Placebo-Treated Patients in Study 1
Adverse Reaction | Placebo; (N=105); % | LUMRYZ 4.5 g; (N=107); % | LUMRYZ 6 g (N=97); % | LUMRYZ 7.5 g; (N=88); % | LUMRYZ 9 g (N=77); %
Gastrointestinal Disorders
Vomiting | 2 | 3 | 3 | 6 | 5
Nausea | 3 | 6 | 8 | 7 | 1
Investigations
Weight Decreased | 0 | 1 | 0 | 0 | 4
Metabolism and Nutritional Disorders
Decreased Appetite | 0 | 4 | 4 | 3 | 3
Nervous System Disorders
Dizziness | 0 | 6 | 4 | 6 | 5
Somnolence | 1 | 0 | 1 | 2 | 4
Headache | 6 | 7 | 5 | 6 | 0
Psychiatric Disorders
Enuresis | 0 | 2 | 4 | 9 | 9
Anxiety | 1 | 3 | 1 | 3 | 1
Somnambulism | 0 | 1 | 2 | 0 | 0

Dose-Response Information

In the clinical trial in adult patients with narcolepsy, a dose-response relationship was observed for enuresis and somnolence.

Additional Adverse Reactions

Adverse reactions observed in clinical studies with immediate-release sodium oxybate (≥2%), but not observed in Study 1 at a frequency of higher than 2%, and which may be relevant for LUMRYZ: diarrhea, abdominal pain upper, dry mouth, pain, feeling drunk, peripheral edema, cataplexy, muscle spasms, pain in extremity, tremor, disturbance in attention, paresthesia, sleep paralysis, disorientation, irritability, and hyperhidrosis.

Pediatric Patients (7 Years of Age and Older)

The safety of LUMRYZ for the treatment of cataplexy or excessive daytime sleepiness in pediatric patients 7 years of age and older with narcolepsy is supported by an adequate and well-controlled trial of immediate-release sodium oxybate [see Clinical Studies (14.2)]. Below is a display of adverse reactions of immediate-release sodium oxybate in this adequate and well-controlled trial.

In this trial, 104 patients aged 7 to 17 years (37 patients aged 7 to 11 years; 67 patients aged 12 to 17 years) with narcolepsy received immediate-release sodium oxybate for up to one year. This trial included an open-label safety continuation period in which eligible patients received immediate-release sodium oxybate for up to an additional 2 years. The median and maximum exposure across the entire trial were 371 and 987 days, respectively.

Adverse Reactions Leading to Treatment Discontinuation

In the pediatric clinical trial with immediate-release sodium oxybate, 7 of 104 patients reported adverse reactions that led to withdrawal from the study (hallucination, tactile; suicidal ideation; weight decreased; sleep apnea syndrome; affect lability; anger, anxiety, depression; and headache).

Adverse Reactions in the Pediatric Clinical Trial

The most common adverse reactions (≥5%) were nausea (20%), enuresis (19%), vomiting (18%), headache (17%), weight decreased (13%), decreased appetite (9%), dizziness (8%), and sleepwalking (6%).

Additional information regarding safety in pediatric patients appears in the following sections:

● Respiratory Depression and Sleep-Disordered Breathing [see Warnings and Precautions (5.4)]

● Depression and Suicidality [see Warnings and Precautions (5.5)]

● Other Behavioral or Psychiatric Adverse Reactions [see Warnings and Precautions (5.6)]

● Parasomnias [see Warnings and Precautions (5.7)]

The overall adverse reaction profile of immediate-release sodium oxybate in the pediatric clinical trial was similar to that seen in the adult clinical trial with immediate-release sodium oxybate. The safety profile in pediatric patients with LUMRYZ is expected to be similar to that of adult patients treated with LUMRYZ and to that of pediatric patients treated with immediate-release sodium oxybate.

6.2 Postmarketing Experience

The following adverse reactions have been identified during postapproval use of sodium oxybate. Because these reactions are reported voluntarily from a population of uncertain size, it is not always possible to reliably estimate their frequency or establish a causal relationship to drug exposure:

Arthralgia, decreased appetite, fall*, fluid retention, hangover, headache, hypersensitivity, hypertension, memory impairment, nocturia, panic attack, vision blurred, and weight decreased.

*The sudden onset of sleep in patients taking sodium oxybate, including in a standing position or while rising from bed, has led to falls complicated by injuries, in some cases requiring hospitalization.

7 DRUG INTERACTIONS

7.1 Alcohol, Sedative Hypnotics, and CNS Depressants

LUMRYZ is contraindicated for use in combination with alcohol or sedative hypnotics. Use of other CNS depressants may potentiate the CNS-depressant effects of LUMRYZ [see Warnings and Precautions (5.1)]. In addition to coadministration of LUMRYZ and alcohol being contraindicated because of respiratory depression, consumption of alcohol while taking LUMRYZ may also result in a more rapid release of the dose of sodium oxybate [see Clinical Pharmacology (12.3)].

8 USE IN SPECIFIC POPULATIONS

8.1 Pregnancy

Risk Summary

There are no adequate data on the developmental risk associated with the use of sodium oxybate in pregnant women. Oral administration of sodium oxybate to pregnant rats (150, 350, or 1,000 mg/kg/day) or rabbits (300, 600, or 1,200 mg/kg/day) throughout organogenesis produced no clear evidence of developmental toxicity; however, oral administration to rats throughout pregnancy and lactation resulted in increased stillbirths and decreased offspring postnatal viability and growth, at a clinically relevant dose [see Data].

In the U.S. general population, the estimated background risk of major birth defects and miscarriage in clinically recognized pregnancies is 2 to 4% and 15 to 20%, respectively. The background risk of major birth defects and miscarriage for the indicated population is unknown.

Clinical Considerations

Labor or Delivery

LUMRYZ has not been studied in labor or delivery. In obstetric anesthesia using an injectable formulation of sodium oxybate, newborns had stable cardiovascular and respiratory measures but were very sleepy, causing a slight decrease in Apgar scores. There was a fall in the rate of uterine contractions 20 minutes after injection. Placental transfer is rapid and gamma-hydroxybutyrate (GHB) has been detected in newborns at delivery after intravenous administration of GHB to mothers. Subsequent effects of sodium oxybate on later growth, development, and maturation in humans are unknown.

Data

Animal Data

Oral administration of sodium oxybate to pregnant rats (150, 350, or 1,000 mg/kg/day) or rabbits (300, 600, or 1,200 mg/kg/day) throughout organogenesis produced no clear evidence of developmental toxicity. The highest doses tested in rats and rabbits were approximately 1 and 3 times, respectively, the maximum recommended human dose (MRHD) of 9 g per night on a body surface area (mg/m^2) basis.

Oral administration of sodium oxybate (150, 350, or 1,000 mg/kg/day) to rats throughout pregnancy and lactation resulted in increased stillbirths and decreased offspring postnatal viability and body weight gain at the highest dose tested. The no-effect dose for pre- and postnatal developmental toxicity in rats is less than the MRHD on a mg/m^2 basis.

8.2 Lactation

Risk Summary

GHB is excreted in human milk after oral administration of sodium oxybate. There is insufficient information on the risk to a breastfed infant, and there is insufficient information on milk production in nursing mothers. The developmental and health benefits of breastfeeding should be considered along with the mother’s clinical need for LUMRYZ and any potential adverse effects on the breastfed infant from LUMRYZ or from the underlying maternal condition.

8.4 Pediatric Use

LUMRYZ has not been studied in a pediatric clinical trial. The safety and effectiveness of LUMRYZ in the treatment of cataplexy or excessive daytime sleepiness in pediatric patients 7 years of age and older with narcolepsy is supported by evidence from a double-blind, placebo-controlled, randomized-withdrawal study of immediate-release sodium oxybate [see Adverse Reactions (6.1) and Clinical Studies (14.2)].

In the pediatric clinical trial with immediate-release sodium oxybate administration in pediatric patients 7 years of age and older with narcolepsy, serious adverse reactions of central sleep apnea and oxygen desaturation documented by polysomnography evaluation; depression; suicidal ideation; neuropsychiatric reactions including acute psychosis, confusion, and anxiety; and parasomnias, including sleepwalking, have been reported [see Warnings and Precautions (5.4, 5.5, 5.6, 5.7) and Adverse Reactions (6.1)].

The safety and effectiveness of LUMRYZ have not been established in pediatric patients younger than 7 years old.

Juvenile Animal Toxicity Data

In a study in which sodium oxybate (0, 100, 300, or 900 mg/kg/day) was orally administered to rats during the juvenile period of development (postnatal days 21 through 90), mortality was observed at the two highest doses tested. Deaths occurred during the first week of dosing and were associated with clinical signs (including decreased activity and respiratory rate) consistent with the pharmacological effects of the drug. Reduced body weight gain in males and females and delayed sexual maturation in males were observed at the highest dose tested. The no-effect dose for adverse effects in juvenile rats is associated with plasma exposures (AUC) less than that at the maximum recommended human dose (9 g/night).

8.5 Geriatric Use

Clinical studies of LUMRYZ or immediate-release sodium oxybate in patients with narcolepsy did not include sufficient numbers of subjects age 65 years and older to determine whether they respond differently from younger subjects. In controlled trials of immediate-release sodium oxybate in another population, 39 (5%) of 874 patients were 65 years or older. Discontinuations of treatment due to adverse reactions were increased in the elderly compared to younger adults (21% vs. 19%). Frequency of headaches was markedly increased in the elderly (39% vs. 19%). The most common adverse reactions were similar in both age categories. In general, dose selection for an elderly patient should be cautious, usually starting at the low end of the dosing range, reflecting the greater frequency of decreased hepatic, renal, or cardiac function, and of concomitant disease or other drug therapy.

8.6 Hepatic Impairment

Because of an increase in exposure to LUMRYZ, LUMRYZ should not be initiated in patients with hepatic impairment because appropriate dosage adjustments for initiation of LUMRYZ cannot be made with the available dosage strengths [see Clinical Pharmacology (12.3)]. Patients with hepatic impairment who have been titrated to a maintenance dosage of another oxybate product can be switched to LUMRYZ if the appropriate dosage strength is available.

9 DRUG ABUSE AND DEPENDENCE

9.1 Controlled Substance

LUMRYZ is a Schedule III controlled substance under the Federal Controlled Substances Act. Non-medical use of LUMRYZ could lead to penalties assessed under the higher Schedule I controls.

9.2 Abuse

LUMRYZ (sodium oxybate), the sodium salt of GHB, produces dose-dependent central nervous system effects, including hypnotic and positive subjective reinforcing effects. The onset of effect is rapid, enhancing its potential for abuse or misuse.

Drug abuse is the intentional non-therapeutic use of a drug product or substance, even once, for its desirable psychological or physiological effects. Misuse is the intentional use, for therapeutic purposes of a drug by an individual in a way other than prescribed by a healthcare provider or for whom it was not prescribed. Drug misuse and abuse may occur with or without progression to addiction. Drug addiction is a cluster of behavioral, cognitive, and physiological phenomena that may include a strong desire to take the drug, difficulties in controlling drug use (e.g., continuing drug use despite harmful consequences, giving a higher priority to drug use than other activities and obligations), and possible tolerance or physical dependence.

The rapid onset of sedation, coupled with the amnestic features of GHB, particularly when combined with alcohol, has proven to be dangerous for the voluntary and involuntary user (e.g., assault victim).

Illicit GHB is abused in social settings primarily by young adults. Some of the doses estimated to be abused are in a similar dosage range to that used for treatment of patients with cataplexy. GHB has some commonalities with ethanol over a limited dose range, and some cross tolerance with ethanol has been reported as well. Cases of severe dependence and craving for GHB have been reported when the drug is taken around the clock. Patterns of abuse indicative of dependence include: 1) the use of increasingly large doses, 2) increased frequency of use, and 3) continued use despite adverse consequences.

Because illicit use and abuse of GHB have been reported, physicians should carefully evaluate patients for a history of drug abuse and follow such patients closely, observing them for signs of misuse or abuse of GHB (e.g., increase in size or frequency of dosing, drug-seeking behavior, feigned cataplexy). Dispose of LUMRYZ according to state and federal regulations. It is safe to dispose of LUMRYZ down the sanitary sewer.

9.3 Dependence

Dependence

Physical dependence is a state that develops as a result of physiological adaptation in response to repeated drug use, manifested by withdrawal signs and symptoms after abrupt discontinuation or a significant dose reduction of a drug. There have been case reports of withdrawal, ranging from mild to severe, following discontinuation of illicit use of GHB at frequent repeated doses (18 g to 250 g per day) in excess of the recommended dosage range. Signs and symptoms of GHB withdrawal following abrupt discontinuation included insomnia, restlessness, anxiety, psychosis, lethargy, nausea, tremor, sweating, muscle cramps, tachycardia, headache, dizziness, rebound fatigue and sleepiness, confusion, and, particularly in the case of severe withdrawal, visual hallucinations, agitation, and delirium. These symptoms generally abated in 3 to 14 days. In cases of severe withdrawal, hospitalization may be required. The discontinuation effects of LUMRYZ have not been systematically evaluated in controlled clinical trials. In the clinical trial experience with immediate-release sodium oxybate in narcolepsy/cataplexy patients at recommended doses, two patients reported anxiety and one reported insomnia following abrupt discontinuation at the termination of the clinical trial; in the two patients with anxiety, the frequency of cataplexy had increased markedly at the same time.

Tolerance

Tolerance is a physiological state characterized by a reduced response to a drug after repeated administration (i.e., a higher dose of a drug is required to produce the same effect that was once obtained at a lower dose). Tolerance to LUMRYZ has not been systematically studied in controlled clinical trials. There have been some case reports of symptoms of tolerance developing after illicit use at dosages far in excess of the recommended LUMRYZ dosage regimen. Clinical studies of immediate-release sodium oxybate in the treatment of alcohol withdrawal suggest a potential cross-tolerance with alcohol. The safety and effectiveness of LUMRYZ in the treatment of alcohol withdrawal have not been established.

10 OVERDOSAGE

10.1 Human Experience

Information regarding overdose with LUMRYZ is derived largely from reports in the medical literature that describe symptoms and signs in individuals who have ingested GHB illicitly. In these circumstances, the co-ingestion of other drugs and alcohol was common and may have influenced the presentation and severity of clinical manifestations of overdose.

In adult clinical trials of immediate-release sodium oxybate, two cases of overdose with sodium oxybate were reported. In the first case, an estimated dose of 150 g, more than 15 times the maximum recommended dose, caused a patient to be unresponsive with brief periods of apnea and to be incontinent of urine and feces. This individual recovered without sequelae. In the second case, death was reported following a multiple drug overdose consisting of sodium oxybate and numerous other drugs.

10.2 Signs and Symptoms

Information about signs and symptoms associated with overdosage with LUMRYZ derives from reports of illicit use of GHB. Patient presentation following overdose is influenced by the dose ingested, the time since ingestion, the co-ingestion of other drugs and alcohol, and the fed or fasted state. Patients have exhibited varying degrees of depressed consciousness that may fluctuate rapidly between a confusional, agitated combative state with ataxia and coma. Emesis (even when obtunded), diaphoresis, headache, and impaired psychomotor skills have been observed. No typical pupillary changes have been described to assist in diagnosis; pupillary reactivity to light is maintained. Blurred vision has been reported. An increasing depth of coma and acidosis have been observed at higher doses. Myoclonus and tonic-clonic seizures have been reported.

Respiration may be unaffected or compromised in rate and depth. Cheyne-Stokes respiration and apnea have been observed. Bradycardia and hypothermia may accompany unconsciousness, as well as muscular hypotonia, but tendon reflexes remain intact.

10.3 Recommended Treatment of Overdose

General symptomatic and supportive care should be instituted immediately, and gastric decontamination may be considered if co-ingestants are suspected. Because emesis may occur in the presence of obtundation, appropriate posture (left lateral recumbent position) and protection of the airway by intubation may be warranted. Although the gag reflex may be absent in deeply comatose patients, even unconscious patients may become combative to intubation, and rapid-sequence induction (without the use of sedative) should be considered. Vital signs and consciousness should be closely monitored. The bradycardia reported with GHB overdose has been responsive to atropine intravenous administration. No reversal of the central depressant effects of LUMRYZ can be expected from naloxone or flumazenil administration. The use of hemodialysis and other forms of extracorporeal drug removal have not been studied in GHB overdose, but have been reported in cases of acidosis associated with GHB ingestions of 125 g or greater; however, due to the rapid metabolism of sodium oxybate, these measures may not be warranted.

10.4 Poison Control Center

As with the management of all cases of drug overdosage, the possibility of multiple drug ingestion should be considered. The healthcare provider is encouraged to collect urine and blood samples for routine toxicologic screening, and to consult with a regional poison control center (1-800-222-1222) for current treatment recommendations.

11 DESCRIPTION

Sodium oxybate, a CNS depressant, is the active ingredient in LUMRYZ for extended-release oral suspension. The chemical name for sodium oxybate is sodium 4-hydroxybutyrate. The molecular formula is C4H7NaO3, and the molecular weight is 126.09 g/mole. The chemical structure is:

Sodium oxybate is a white to off-white solid powder.

Each packet of LUMRYZ contains 4.5 g, 6 g, 7.5 g, or 9 g of sodium oxybate, equivalent to 3.7 g, 5.0 g, 6.2 g, or 7.4 g of oxybate, respectively. The inactive ingredients are carrageenan, hydrogenated vegetable oil, hydroxyethyl cellulose, magnesium stearate, malic acid, methacrylic acid copolymer, microcrystalline cellulose, povidone, and xanthan gum.

12 CLINICAL PHARMACOLOGY

12.1 Mechanism of Action

LUMRYZ is a CNS depressant. The mechanism of action of LUMRYZ in the treatment of narcolepsy is unknown. Sodium oxybate is the sodium salt of gamma-hydroxybutyrate (GHB), an endogenous compound and metabolite of the neurotransmitter GABA. It is hypothesized that the therapeutic effects of LUMRYZ on cataplexy and excessive daytime sleepiness are mediated through GABAB actions at noradrenergic and dopaminergic neurons, as well as at thalamocortical neurons.

12.3 Pharmacokinetics

Following oral administration of LUMRYZ, the plasma levels of GHB increased dose-proportionally for Cmax and more than dose-proportionally for area under the plasma concentration-time curve (AUCinf) (respectively, 2-fold and 2.3-fold increases as total daily dose is doubled from 4.5 g to 9 g).

No clinically significant difference in oxybate pharmacokinetics was observed between a single 6 g dose of LUMRYZ and two 3 g doses of immediate-release sodium oxybate administered 4 hours apart.

Absorption

Following oral administration of a single 6 g dose of LUMRYZ, the peak plasma concentration (Cmax) was 66 mcg/mL and the time to peak plasma concentration (Tmax) was 1.5 hours.

Effect of Food

Administration of LUMRYZ immediately after a high-fat meal resulted in a mean reduction in Cmax and AUC of GHB by 33% and 14%, respectively; average Tmax increased from 0.5 hours to 1.5 hours [see Dosage and Administration (2.3)].

Effect of Ethanol

An in vitro study showed alcohol-induced dose-dumping of sodium oxybate from extended-release oral suspension at 1 hour in the presence of 40% alcohol, and approximately 60% increase of drug release at 2 hours in the presence of 20% alcohol [see Contraindications (4) and Warnings and Precautions (5.1)].

Effect of Water Temperature

An in vitro dissolution study showed that LUMRYZ mixed with hot water (90°C) resulted in a dose-dumping phenomenon for the release of sodium oxybate, whereas warm water (50°C) did not significantly affect the drug release from the extended-release suspension [see Dosage and Administration (2.3)].

Effect of Water Flavoring

An in vitro dissolution study showed that LUMRYZ mixed with water prepared with calorie-free drink mix (e.g., Crystal Light Raspberry Lemonade Drink Mix) or flavored water enhancer (e.g., Mio Fruit Punch Concentrate Liquid Water Enhancer) did not impact the drug release from the extended-release suspension [see Dosage and Administration (2.3)].

Distribution

GHB is a hydrophilic compound with an apparent volume of distribution averaging 190 mL/kg to 384 mL/kg. At GHB concentrations ranging from 3 mcg/mL to 300 mcg/mL, less than 1% is bound to plasma proteins.

Elimination

Metabolism

Animal studies indicate that metabolism is the major elimination pathway for GHB, producing carbon dioxide and water via the tricarboxylic acid (Krebs) cycle, and secondarily by β-oxidation. The primary pathway involves a cytosolic NADP^+-linked enzyme, GHB dehydrogenase, which catalyzes the conversion of GHB to succinic semialdehyde, which is then biotransformed to succinic acid by the enzyme succinic semialdehyde dehydrogenase. Succinic acid enters the Krebs cycle where it is metabolized to carbon dioxide and water. A second mitochondrial oxidoreductase enzyme, a transhydrogenase, also catalyzes the conversion to succinic semialdehyde in the presence of α-ketoglutarate. An alternate pathway of biotransformation involves β-oxidation via 3,4-dihydroxybutyrate to carbon dioxide and water. No active metabolites have been identified.

Excretion

The clearance of GHB is almost entirely by biotransformation to carbon dioxide, which is then eliminated by expiration. On average, less than 5% of unchanged drug appears in human urine within 6 to 8 hours after dosing. Fecal excretion is negligible. GHB has an elimination half-life of 0.5 to 1 hour.

Specific Population

Geriatric Patients

There is limited experience with LUMRYZ in the elderly. Results from a pharmacokinetic study of immediate-release sodium oxybate (n=20) in another studied population indicate that the pharmacokinetic characteristics of GHB are consistent among younger (age 48 to 64 years) and older (age 65 to 75 years) adults.

Pediatric Patients

The pharmacokinetics of LUMRYZ has not been directly evaluated in pediatric patients.

The pharmacokinetics of immediate-release sodium oxybate were evaluated in pediatric patients 7 to 17 years of age (n=29). The pharmacokinetic characteristics of immediate-release sodium oxybate were shown to be similar in adults and pediatric patients. Body weight was found to be the major intrinsic factor affecting oxybate pharmacokinetics.

Male and Female Patients

In a study of 18 female and 18 male healthy adult volunteers, no gender differences were detected in the pharmacokinetics of GHB following an immediate-release 4.5 g oral dose of sodium oxybate.

Racial or Ethnic Groups

There are insufficient data to evaluate any pharmacokinetic differences among races.

Patients with Renal Impairment

No pharmacokinetic study in patients with renal impairment has been conducted.

Patients with Hepatic Impairment

The pharmacokinetics of GHB in 16 cirrhotic patients, half without ascites (Child’s Class A) and half with ascites (Child’s Class C), were compared to the kinetics in 8 subjects with normal hepatic function, after a single sodium oxybate oral dose of 25 mg/kg. AUC values were doubled in cirrhotic patients, with apparent oral clearance reduced from 9.1 mL/min/kg in healthy adults to 4.5 and 4.1 mL/min/kg in Class A and Class C patients, respectively. Elimination half-life was significantly longer in Class C and Class A patients than in control patients (mean t1/2 of 59 minutes and 32 minutes, respectively, versus 22 minutes in control patients). LUMRYZ should not be initiated in patients with liver impairment [see Use in Specific Populations (8.6)].

Drug Interaction Studies

In vitro studies with pooled human liver microsomes indicate that sodium oxybate does not significantly inhibit the activities of the human isoenzymes CYP1A2, CYP2C9, CYP2C19, CYP2D6, CYP2E1, or CYP3A, up to the concentration of 3 mM (378 mcg/mL), a level considerably higher than levels achieved with the maximum recommended dose.

A drug interaction study in healthy adults (age 18 to 55 years) was conducted with LUMRYZ and divalproex sodium. Co-administration of a single dose of LUMRYZ (6 g) with divalproex sodium ER at steady state resulted in an approximate 18% increase in AUC (90% CI ratio range of 112%-123%), which is not expected to be clinically meaningful, while Cmax was comparable. A single dose of LUMRYZ (6 g) did not appear to affect the pharmacokinetics of divalproex sodium. However, a pharmacodynamic interaction between LUMRYZ and divalproex sodium, a sedative antiepileptic drug, cannot be ruled out [see Warnings and Precautions (5.1) and Drug Interactions (7.1)].

Drug interaction studies in healthy adults (age 18 to 50 years) were conducted with immediate-release sodium oxybate and diclofenac and ibuprofen:

● Diclofenac: Co-administration of sodium oxybate (6 g per day as two equal doses of 3 grams dosed four hours apart) with diclofenac (50 mg/dose twice per day) showed no significant changes in systemic exposure to GHB. Co-administration did not appear to affect the pharmacokinetics of diclofenac.

● Ibuprofen: Co-administration of sodium oxybate (6 g per day as two equal doses of 3 grams dosed four hours apart) with ibuprofen (800 mg/dose four times per day also dosed four hours apart) resulted in comparable systemic exposure to GHB, as shown by plasma Cmax and AUC values. Co-administration did not affect the pharmacokinetics of ibuprofen.

Drug interaction studies in healthy adults demonstrated no pharmacokinetic interactions between immediate-release sodium oxybate and protriptyline hydrochloride, zolpidem tartrate, and modafinil. Also, there were no pharmacokinetic interactions with the alcohol dehydrogenase inhibitor fomepizole. However, pharmacodynamic interactions with these drugs cannot be ruled out. Alteration of gastric pH with omeprazole produced no significant change in the pharmacokinetics of GHB. In addition, drug interaction studies in healthy adults demonstrated no pharmacokinetic or clinically significant pharmacodynamic interactions between immediate-release sodium oxybate and duloxetine HCl.

13 NONCLINICAL TOXICOLOGY

13.1 Carcinogenesis, Mutagenesis, Impairment of Fertility

Carcinogenesis

Administration of sodium oxybate to rats at oral doses of up to 1,000 mg/kg/day for 83 (males) or 104 (females) weeks resulted in no increase in tumors. Plasma exposure (AUC) at the highest dose tested was 2 times that in humans at the maximum recommended human dose (MRHD) of 9 g per night.

The results of 2-year carcinogenicity studies in mouse and rat with gamma-butyrolactone, a compound that is metabolized to sodium oxybate in vivo, showed no clear evidence of carcinogenic activity. The plasma AUCs of sodium oxybate achieved at the highest doses tested in these studies were less than that in humans at the MRHD.

Mutagenesis

Sodium oxybate was negative in the in vitro bacterial gene mutation assay, an in vitro chromosomal aberration assay in mammalian cells, and in an in vivo rat micronucleus assay.

Impairment of Fertility

Oral administration of sodium oxybate (150, 350, or 1,000 mg/kg/day) to male and female rats prior to and throughout mating and continuing in females through early gestation resulted in no adverse effects on fertility. The highest dose tested is approximately equal to the MRHD on a mg/m^2 basis.

14 CLINICAL STUDIES

14.1 Cataplexy and Excessive Daytime Sleepiness (EDS) in Adult Narcolepsy

The effectiveness of LUMRYZ for the treatment of cataplexy or excessive daytime sleepiness (EDS) in adults with narcolepsy has been established based on a double-blind, randomized, placebo-controlled, two-arm multi-center study to assess the efficacy and safety of a once nightly administration of LUMRYZ in patients with narcolepsy (Study 1; NCT02720744).

A total of 212 patients were randomized to receive LUMRYZ or placebo in a 1:1 ratio and received at least one dose of study drug. The study was divided into four sequential study periods, and incorporated dose titration to stabilized dose administration of LUMRYZ (4.5 g, 6 g, 7.5 g, and 9 g). There was a three-week screening period, a 13-week treatment period including up-titration over a period of eight weeks, five weeks of stable dosing at 9 g/night, and a one-week follow-up period. Patients could be on concomitant stimulant as long as dosage was stable for 3 weeks prior to study start.

The three co-primary endpoints were the Maintenance of Wakefulness Test (MWT), Clinical Global Impression-Improvement (CGI-I), and mean change in weekly cataplexy attacks. The MWT measures latency to sleep onset (in minutes), averaged over five sessions at 2-hour intervals following nocturnal polysomnography. For each test session, patients were instructed to remain awake for as long as possible during 30-minute test sessions, and sleep latency was determined as the number of minutes patients could remain awake. The overall score was the mean sleep latency for the 5 sessions. The CGI-I was evaluated on a 7-point scale, centered at No Change, and ranging from Very Much Worse to Very Much Improved. Patients were rated by evaluators who based their assessments on the severity of narcolepsy at Baseline.

Demographic and mean baseline characteristics were similar for the LUMRYZ and placebo groups. A total of 76% were narcolepsy type 1 (NT1; with both symptoms of EDS and cataplexy) patients, and 24% were narcolepsy type 2 (NT2; with symptoms of EDS and without cataplexy) patients. The mean age was 31 years, and 68% were female. Approximately 63% of patients were on concomitant stimulant use. The mean MWT at baseline was 5 minutes for the LUMRYZ group, and 4.7 minutes for the placebo group. The mean number of cataplexy attacks per week at baseline was 18.9 in the LUMRYZ group and 19.8 in the placebo group. A statistically significant improvement was seen on the MWT, CGI-I, and mean weekly cataplexy attacks, for the 6 g (Week 3), 7.5 g (Week 8), and 9 g (Week 13) dose of LUMRYZ, compared to the placebo group (see Table 3, Table 4, and Table 5).

Table 3: Change from Baseline in the Maintenance of Wakefulness Test
Dose | Treatment Group (N) | Change from Baseline (Minutes)* | Difference from Placebo [95% CI] | p-value
6 g (Week 3) | LUMRYZ (87) | 8.1 | 5.0 [2.90;7.05] | <0.001
6 g (Week 3) | Placebo (88) | 3.1 | - | -
7.5 g (Week 8) | LUMRYZ (76) | 9.6 | 6.2 [3.84;8.58] | <0.001
7.5 g (Week 8) | Placebo (78) | 3.3 | - | -
9 g (Week 13) | LUMRYZ (68) | 10.8 | 6.1 [3.52;8.75] | <0.001
9 g (Week 13) | Placebo (78) | 4.7 | - | -
*Mean MWT at baseline was 5.0 minutes for the LUMRYZ group and 4.7 minutes for the placebo group

Table 4: Proportion of Patients with a Very Much or Much Improved Clinical Global Impression-Improvement
Dose | Treatment Group (N) | Percentage of Responders (Much or Very Much Improved) | Odds Ratio [95% CI] | p-value
6 g (Week 3) | LUMRYZ (87) | 40 | 10.3 [3.93;26.92] | <0.001
6 g (Week 3) | Placebo (87) | 6 | - | -
7.5 g (Week 8) | LUMRYZ (75) | 64 | 5.7 [2.82;11.40] | <0.001
7.5 g (Week 8) | Placebo (81) | 22 | - | -
9 g (Week 13) | LUMRYZ (69) | 73 | 5.6 [2.76;11.23] | <0.001
9 g (Week 13) | Placebo (79) | 32 | - | -

Table 5: Change from Baseline in the Mean Cataplexy Attacks Per Week in NT1 Patients
Dose | Treatment Group (N) | Change from Baseline* | Difference from Placebo [95% CI] | p-value
6 g (Week 3) | LUMRYZ (73) | -7.4 | -4.8 [-7.03;-2.62] | <0.001
6 g (Week 3) | Placebo (72) | -2.6 | - | -
7.5 g (Week 8) | LUMRYZ (66) | -10.0 | -6.3 [-8.74;-3.80] | <0.001
7.5 g (Week 8) | Placebo (69) | -3.7 | - | -
9 g (Week 13) | LUMRYZ (55) | -11.5 | -6.7 [-9.32;-3.98] | <0.001
9 g (Week 13) | Placebo (62) | -4.9 | - | -
*Mean (SD) number of cataplexy attacks per week at baseline was 18.9 (8.7) in the LUMRYZ group and 19.8 (8.9) in the placebo group

14.2 Cataplexy and Excessive Daytime Sleepiness (EDS) in Pediatric Narcolepsy

The effectiveness of LUMRYZ in pediatric patients is based upon a clinical study in patients treated with immediate-release sodium oxybate, as described below.

The effectiveness of immediate-release sodium oxybate in the treatment of cataplexy or excessive daytime sleepiness in pediatric patients 7 years of age and older with narcolepsy was established in a double-blind, placebo-controlled, randomized-withdrawal study (NCT02221869). The study was conducted in 106 pediatric patients (median age: 12 years; range: 7 to 17 years) with a baseline history of at least 14 cataplexy attacks in a typical 2-week period prior to any treatment for narcolepsy symptoms. Of the 106 patients, 2 did not receive study drug and 63 patients were randomized 1:1 either to continued treatment with immediate-release sodium oxybate or to placebo. Randomization to placebo was stopped early as the efficacy criterion was met at the pre-planned interim analysis.

Patients entered the study either taking a stable dosage of immediate-release sodium oxybate or were immediate-release sodium oxybate-naïve. CNS stimulants were allowed at entry, and approximately 50% of patients continued taking a stable dose of stimulant throughout the stable-dose and double-blind periods. Immediate-release sodium oxybate-naïve patients were initiated and titrated based on body weight over a period of up to 10 weeks. The total nightly dose was administered in two divided doses, with the first dose given at nighttime and the second given 2.5 to 4 hours later. Once a stable dosage of immediate-release sodium oxybate had been achieved, these patients entered the 2-week stable-dose period; patients on a stable dosage of immediate-release sodium oxybate at study entry remained on this dosage for 3 weeks prior to randomization. Efficacy was established at dosages ranging from 3 g to 9 g of immediate-release sodium oxybate per night.

The primary efficacy measure was the change in frequency of cataplexy attacks. In addition, change in cataplexy severity was evaluated with the Clinical Global Impression of Change for cataplexy severity. The Clinical Global Impression of Change is evaluated on a 7-point scale, centered at No Change, and ranging from Very Much Worse to Very Much Improved. The efficacy of immediate-release sodium oxybate in the treatment of excessive daytime sleepiness in pediatric patients with narcolepsy was evaluated with the change in the Epworth Sleepiness Scale (Child and Adolescent) score. The Epworth Sleepiness Scale (Child and Adolescent) is a modified version of the Epworth Sleepiness Scale used in the adult clinical trial with immediate-release sodium oxybate. The Epworth Sleepiness Scale is intended to evaluate the extent of sleepiness in everyday situations by asking the patient a series of questions. In these questions, patients were asked to rate their chances of dozing during each of 8 activities on a scale from 0-3 (0=never; 1=slight; 2=moderate; 3=high). Higher total scores indicate a greater tendency to sleepiness. The overall change in narcolepsy condition was assessed by the Clinical Global Impression of Change for narcolepsy overall. Efficacy was assessed during or at the end of the 2-week double-blind treatment period, relative to the last 2 weeks or end of the stable-dose period (see Tables 6 and 7).

Pediatric patients taking stable dosages of immediate-release sodium oxybate who were withdrawn from immediate-release sodium oxybate treatment and were randomized to placebo during the double-blind treatment period experienced a statistically significant increase in weekly cataplexy attacks compared with patients who were randomized to continue treatment with immediate-release sodium oxybate. Patients randomized to receive placebo during the double-blind treatment period experienced a statistically significant worsening of EDS compared with patients randomized to continue receiving immediate-release sodium oxybate (see Table 6).

Table 6: Number of Weekly Cataplexy Attacks and Epworth Sleepiness Scale (Child and Adolescent) Score
Treatment Group | Baseline*,† | Double-blind Treatment Period‡,§ | Median Change from Baseline | Comparison to Placebo (p-value¶)
Median Number of Cataplexy Attacks (attacks/week)
Placebo (n=32) | 4.7 | 21.3 | 12.7 | -
Immediate-release; Sodium Oxybate (n=31) | 3.5 | 3.8 | 0.3 | <0.0001
Median Epworth Sleepiness Scale (Child and Adolescent) Score
Placebo (n=31**) | 11 | 12 | 3 | -
Immediate-release; Sodium Oxybate (n=30**) | 8 | 9 | 0 | 0.0004
* For weekly number of cataplexy attacks, baseline value is calculated from the last 14 days of the stable-dose period.
† For Epworth Sleepiness Scale score, baseline value is collected at the end of stable-dose period.
‡ Weekly number of cataplexy attacks is calculated from all days within the double-blind treatment period.
§ For Epworth Sleepiness Scale, value is collected at the end of the double-blind treatment period.
¶ P-value from rank-based analysis of covariance (ANCOVA) with treatment as a factor and rank baseline value as a covariate.
** One patient in each of the treatment groups did not have baseline ESS score available and were not included in this analysis.

Patients randomized to receive placebo during the double-blind treatment period experienced a statistically significant worsening of cataplexy severity and narcolepsy overall according to the clinician’s assessment compared with patients randomized to continue receiving immediate-release sodium oxybate (see Table 7).

Table 7: Clinical Global Impression of Change (CGIc) for Cataplexy Severity and Narcolepsy Overall
Worsened, %† | CGIc Cataplexy Severity* |  | CGIc Narcolepsy Overall*
Worsened, %† | Placebo (n=32) | Immediate-release Sodium Oxybate (n=29)‡ | Placebo (n=32) | Immediate-release Sodium Oxybate (n=29)‡
Much worse or very much worse | 66% | 17% | 59% | 10%
p-value§ | 0.0001 |  | <0.0001
* Responses indicate change of severity or symptoms relative to receiving immediate-release sodium oxybate treatment at baseline.
† Percentages based on total number of observed values.
‡ Two patients randomized to immediate-release sodium oxybate did not have the CGIc assessments completed and were excluded from the analysis.
§ P-value from Pearson’s chi-square test.

16 HOW SUPPLIED/STORAGE AND HANDLING

16.1 How Supplied

LUMRYZ is a blend of white to off-white granules for extended-release oral suspension in water. LUMRYZ is supplied in cartons and a 28-day starter pack.

Cartons: each carton contains either 7 or 30 packets of LUMRYZ, a mixing cup, Prescribing Information and Medication Guide, and Instructions for Use (see Table 8). Dose packets contain a single dose of LUMRYZ provided in 4.5 g, 6 g, 7.5 g, or 9 g doses.

Table 8: LUMRYZ Carton Configurations
Strength | Package Size | NDC Number
4.5 g | 7 packets | NDC 13551-001-07
4.5 g | 30 packets | NDC 13551-001-30
6 g | 7 packets | NDC 13551-002-07
6 g | 30 packets | NDC 13551-002-30
7.5 g | 7 packets | NDC 13551-003-07
7.5 g | 30 packets | NDC 13551-003-30
9 g | 7 packets | NDC 13551-004-07
 | 30 packets | NDC 13551-004-30

28-day Starter Pack: contains four 7-count cartons, each containing a mixing cup, Prescribing Information and Medication Guide, and Instructions for Use (see Table 9). Dose packets contain a single dose of LUMRYZ provided in 4.5 g, 6 g, or 7.5 g doses.

Table 9: LUMRYZ Starter Pack Contents
28-day Starter Pack | Strength | Package Size | NDC Number
Week 1 | 4.5 g | 7 packets | NDC 13551-005-01
Week 2 | 6 g | 7 packets | NDC 13551-005-01
Week 3 | 6 g | 7 packets | NDC 13551-005-01
Week 4 | 7.5 g | 7 packets | NDC 13551-005-01

16.2 Storage

Keep out of reach of children.

LUMRYZ should be stored at 20°C to 25°C (68°F to 77°F); excursions permitted to 15°C to 30°C (59°F to 86°F) (see USP Controlled Room Temperature).

Suspensions should be consumed within 30 minutes.

16.3 Handling and Disposal

LUMRYZ is a Schedule III drug under the Controlled Substances Act. LUMRYZ should be handled according to state and federal regulations. It is safe to dispose of LUMRYZ down the sanitary sewer.

17 PATIENT COUNSELING INFORMATION

Advise the patient and/or caregiver to read the FDA-approved patient labeling (Medication Guide and Instructions for Use).

Central Nervous System Depression

Inform patients and/or caregivers that LUMRYZ can cause central nervous system depression, including respiratory depression, hypotension, profound sedation, syncope, and death. Instruct patients to not engage in activities requiring mental alertness or motor coordination, including operating hazardous machinery, for at least 6 hours after taking LUMRYZ. Instruct patients and/or caregivers to inform their healthcare providers of all the medications they take [see Warnings and Precautions (5.1)].

Abuse and Misuse

Inform patients and/or caregivers that the active ingredient of LUMRYZ is gamma-hydroxybutyrate (GHB), which is associated with serious adverse reactions with illicit use and abuse [see Warnings and Precautions (5.2)].

LUMRYZ REMS

LUMRYZ is available only through a restricted program called the LUMRYZ REMS [see Warnings and Precautions (5.3)]. Inform the patient and/or caregiver of the following notable requirements:

● LUMRYZ is dispensed only by pharmacies that are specially certified

● LUMRYZ will be dispensed and shipped only to patients who are enrolled in the LUMRYZ REMS

LUMRYZ is available only from certified pharmacies participating in the program. Therefore, provide patients and/or caregivers with the telephone number and website for information on how to obtain the product.

Alcohol or Sedative Hypnotics

Advise patients and/or caregivers that alcohol and other sedative hypnotics should not be taken with LUMRYZ [see Contraindications (4) and Warnings and Precautions (5.1)].

Sedation

Inform patients and/or caregivers that they are likely to fall asleep quickly after taking LUMRYZ (often within 5 and usually within 15 minutes), but the time it takes to fall asleep can vary from night to night. The sudden onset of sleep, including in a standing position or while rising from bed, has led to falls complicated by injuries, in some cases requiring hospitalization [see Adverse Reactions (6.2)]. Instruct patients and/or caregivers that they should remain in bed following ingestion of their dose [see Dosage and Administration (2.3)].

Food Effects on LUMRYZ

Inform patients and/or caregivers that LUMRYZ should be taken at least 2 hours after eating.

Respiratory Depression and Sleep-Disordered Breathing

Inform patients and/or caregivers that LUMRYZ may impair respiratory drive, especially in patients with compromised respiratory function, and may cause apnea [see Warnings and Precautions (5.4)].

Depression and Suicidality

Instruct patients and/or caregivers to contact a healthcare provider immediately if they develop depressed mood, markedly diminished interest or pleasure in usual activities, significant change in weight and/or appetite, psychomotor agitation or retardation, increased fatigue, feelings of guilt or worthlessness, slowed thinking or impaired concentration, or suicidal ideation [see Warnings and Precautions (5.5)].

Other Behavioral or Psychiatric Adverse Reactions

Inform patients and/or caregivers that LUMRYZ can cause behavioral or psychiatric adverse reactions, including confusion, anxiety, and psychosis. Instruct them to notify their healthcare provider if any of these types of symptoms occur [see Warnings and Precautions (5.6)].

Sleepwalking

Instruct patients and/or caregivers that LUMRYZ has been associated with sleepwalking and other behaviors during sleep, and to contact their healthcare provider if this occurs [see Warnings and Precautions (5.7)].

Sodium Intake

Instruct patients and/or caregivers that LUMRYZ contains a significant amount of sodium and patients who are sensitive to sodium intake (e.g., those with heart failure, hypertension, or renal impairment) should limit their sodium intake [see Warnings and Precautions (5.8)].

Distributed By:

Avadel CNS Pharmaceuticals, LLC
Chesterfield, MO

Protected by U.S. Patent No. D1,032,378

Medication Guide
LUMRYZTM (LOOM rize)
(sodium oxybate)
for extended-release oral suspension, CIII

Read this Medication Guide carefully before you start taking LUMRYZ and each time you get a refill. There may be new information. This information does not take the place of talking to your doctor about your medical condition or treatment.

What is the most important information I should know about LUMRYZ?

● LUMRYZ is a central nervous system (CNS) depressant. Taking LUMRYZ with other CNS depressants such as medicines used to make you fall asleep, including opioid analgesics, benzodiazepines, sedating antidepressants, antipsychotics, sedating anti-epileptic medicines, general anesthetics, muscle relaxants, alcohol, or street drugs, may cause serious medical problems, including:

○ trouble breathing (respiratory depression)

○ low blood pressure (hypotension)

○ changes in alertness (drowsiness)

○ fainting (syncope)

○ death

Ask your doctor if you are not sure if you are taking a medicine listed above.

● LUMRYZ is a federal controlled substance (CIII). The active ingredient of LUMRYZ is a form of gamma-hydroxybutyrate (GHB) that is also a federal controlled substance (CI). Abuse of illegal GHB, either alone or with other CNS depressants may cause serious medical problems, including:

○ seizure

○ trouble breathing (respiratory depression)

○ changes in alertness (drowsiness)

○ coma

○ death

Call your doctor right away if you have any of these serious side effects.

● Anyone who takes LUMRYZ should not do anything that requires them to be fully awake or is dangerous, including driving a car, using heavy machinery, or flying an airplane, for at least 6 hours after taking LUMRYZ. Those activities should not be done until you know how LUMRYZ affects you.

● Keep LUMRYZ in a safe place to prevent abuse and misuse. Selling or giving away LUMRYZ may harm others and is against the law. Tell your doctor if you have ever abused or been dependent on alcohol, prescription medicines, or street drugs.

● Because of the risk of CNS depression, abuse, and misuse, LUMRYZ is available only by prescription and filled through certified pharmacies in the LUMRYZ REMS. You must be enrolled in the LUMRYZ REMS to receive LUMRYZ. For more information on how to receive LUMRYZ, visit www.LUMRYZREMS.com. Before you receive LUMRYZ, your doctor or pharmacist will make sure that you understand how to use LUMRYZ safely and effectively. If you have any questions about LUMRYZ, ask your doctor or call the LUMRYZ REMS at 1-877-453-1029.

What is LUMRYZ?

LUMRYZ is a prescription medicine used in people 7 years of age or older to treat the following symptoms of narcolepsy:

● sudden onset of weak or paralyzed muscles (cataplexy), or

● excessive daytime sleepiness (EDS)

It is not known if LUMRYZ is safe and effective in children under 7 years of age.

Do not take LUMRYZ if you or your child:

● take other sleep medicines or sedatives (medicines that cause sleepiness)

● drink alcohol

● have a rare problem called succinic semialdehyde dehydrogenase deficiency

Before taking LUMRYZ, tell your doctor about all medical conditions, including if you or your child:

● have a history of drug abuse.

● have short periods of not breathing while sleeping (sleep apnea).

● have trouble breathing or have lung problems. You or your child may have a higher chance of having serious breathing problems when taking LUMRYZ.

● have or had depression or have tried to harm yourself. You or your child should be watched carefully for new symptoms of depression.

● have or had behavior or other psychiatric problems such as:

○ anxiety

○ seeing or hearing things that are not real (hallucinations)

○ feeling more suspicious (paranoia)

○ being out of touch with reality (psychosis)

○ acting aggressive

○ agitation

● have liver problems.

● are on a salt-restricted diet. LUMRYZ contains a lot of sodium (salt) and may not be right for you or your child.

● have high blood pressure.

● have heart failure.

● have kidney problems.

● are pregnant or plan to become pregnant. It is not known if LUMRYZ can harm your unborn baby.

● are breastfeeding or plan to breastfeed. LUMRYZ passes into breast milk. You and your doctor should decide if you or your child will take LUMRYZ or breastfeed.

Tell your doctor about all the medicines you or your child take, including prescription and over-the-counter medicines, vitamins, and herbal supplements.

Especially, tell your doctor if you or your child take other medicines to help you or your child sleep (sedatives) or that may make you or your child sleepy, such as some medicines to treat pain, anxiety, depression, or seizures. Know the medicines you or your child takes. Keep a list of them to show your doctor and pharmacist when you or your child get a new medicine.

How should I take or give LUMRYZ?

● Read the Instructions for Use for detailed instructions on how to take or give LUMRYZ.

● Take or give LUMRYZ exactly as your doctor tells you to take or give it.

● LUMRYZ is taken by mouth 1 time at bedtime.

● Wait at least 2 hours after eating before taking or giving LUMRYZ.

● After mixing LUMRYZ, take or give it within 30 minutes. Do not mix LUMRYZ with hot water.

● Take or give LUMRYZ at bedtime while you or your child is in bed and lie down immediately. You or your child should remain in bed after taking LUMRYZ.

● LUMRYZ can cause physical dependence and craving for the medicine when it is not taken as directed.

● Never change the LUMRYZ dose without talking to your or your child's doctor.

● LUMRYZ can cause sleep very quickly without feeling drowsy. Some people fall asleep within 5 minutes and most fall asleep within 15 minutes. The time it takes to fall asleep might be different from night to night.

● Falling asleep quickly, including while standing or while getting up from the bed, has led to falls with injuries that have required some people to be hospitalized.

● If you or your child take too much LUMRYZ, call your doctor or go to the nearest hospital emergency room right away.

What are the possible side effects of LUMRYZ?

LUMRYZ can cause serious side effects, including:

● See “What is the most important information I should know about LUMRYZ?”

● breathing problems, including:

○ slower breathing.

○ trouble breathing.

○ short periods of not breathing while sleeping (sleep apnea).

People who already have breathing or lung problems have a higher chance of having breathing problems when they use LUMRYZ.

● mental health problems, including:

○ confusion

○ seeing or hearing things that are not real (hallucinations)

○ unusual or disturbing thoughts (abnormal thinking)

○ feeling anxious or upset

○ depression

○ thoughts of killing yourself or trying to kill yourself

○ increased tiredness

○ feelings of guilt or worthlessness

○ difficulty concentrating

Call your doctor right away if you or your child has symptoms of mental health problems, or a change in weight or appetite.

● sleepwalking. Sleepwalking can cause injuries. Call your doctor if you start or your child starts sleepwalking. Your doctor should check you or your child.

The most common side effects of LUMRYZ in adults include:

● nausea

● dizziness

● bedwetting

● headache

● vomiting

The most common side effects of LUMRYZ in children 7 years of age and older include:

● nausea ● decreased weight

● bedwetting ● decreased appetite

● vomiting ● dizziness

● headache ● sleepwalking

Side effects may increase when taking higher doses of LUMRYZ.

These are not all the possible side effects of LUMRYZ. For more information, ask your doctor or pharmacist. Call your doctor for medical advice about side effects. You may report side effects to FDA at 1-800-FDA-1088.

How should I store LUMRYZ?

● Store LUMRYZ at room temperature between 68°F to 77°F (20°C to 25°C).

● Store LUMRYZ in the original packet prior to mixing with water.

● LUMRYZ suspension should be taken within 30 minutes of preparation.

● When you have finished using the LUMRYZ packet, throw it away (dispose of it) in the trash. If any LUMRYZ remains in the packet, rinse it down the sink before throwing away.

Keep LUMRYZ and all medicines out of the reach of children and pets.

General information about the safe and effective use of LUMRYZ.

Medicines are sometimes prescribed for purposes other than those listed in a Medication Guide. Do not use LUMRYZ for a condition for which it was not prescribed. Do not give LUMRYZ to other people, even if they have the same symptoms. It may harm them.

You can ask your pharmacist or doctor for information about LUMRYZ that is written for health professionals.

What are the ingredients in LUMRYZ?

Active ingredients: sodium oxybate

Inactive ingredients: carrageenan, hydrogenated vegetable oil, hydroxyethyl cellulose, magnesium stearate, malic acid, methacrylic acid copolymer, microcrystalline cellulose, povidone, xanthan gum.

Distributed By:

Avadel CNS Pharmaceuticals, LLC Chesterfield, MO 63005

For more information, go to www.LUMRYZREMS.com or call the LUMRYZ REMS at 1-877-453-1029.

This Medication Guide has been approved by the U.S. Food and Drug Administration. Revised: 10/2024

INSTRUCTIONS FOR USE

This Instructions for Use contains information on how to take LUMRYZ. Read this Instructions for Use before you (or your child) take LUMRYZ and each time you (or your child) get a refill. There may be new information.

This information does not take the place of talking to your doctor about your (or your child's) medical condition or your (or your child's) treatment. If you have questions, please talk with your doctor.

● Take (or give) 1 packet of LUMRYZ each day at bedtime.

● You will need to mix LUMRYZ with water before you take or give your child the dose.

● You (or your child) should avoid getting out of bed after taking LUMRYZ. Some people fall asleep within 5 minutes of taking LUMRYZ and most will fall asleep within 15 minutes. The time it takes to fall asleep might be different from night to night.

● Medicines that cause sleepiness should not be used while taking LUMRYZ.

● Do not use LUMRYZ with alcohol.

● Do not drive or operate heavy machinery within 6 hours of taking LUMRYZ. Those activities should not be done until you know how LUMRYZ affects you.

● Mix and take (or give) LUMRYZ within 30 minutes. If not taken or given within 30 minutes of mixing, throw it away (dispose of it) and prepare a new dose.

LUMRYZ comes in different package sizes. The LUMRYZ package you receive may look different from the picture shown above.

Additional supplies needed

● Store LUMRYZ at room temperature, between 68°F to 77°F (20°C to 25°C).

● Store LUMRYZ in the original packet prior to mixing with water.

● LUMRYZ suspension should be taken within 30 minutes of preparation.

● When you have finished using the LUMRYZ packet, throw it away (dispose of it) in the trash. If any LUMRYZ remains in the packet, rinse it down the sink before throwing away.

● Store LUMRYZ and all medicines out of the reach of children and pets.

● Before using a new LUMRYZ carton, check the tamper-evident seal on the carton lid to make sure it is not missing or broken.

● Do not use if the tamper-evident seal is missing or broken.

● Check the expiration date (EXP) on the LUMRYZ carton.

● Do not use LUMRYZ after the expiration date (EXP) on the label has passed.

● Open the LUMRYZ carton by tearing the tamper-evident seal with your hands or by using a pair of scissors.

● Clean the mixing cup by rinsing it with water and letting it dry before each use.

● Do not use a measuring device other than the mixing cup that comes in your LUMRYZ carton to measure and take a dose of LUMRYZ.

● Check the expiration date (EXP) on the packet label. Do not use the LUMRYZ packet after the expiration date (EXP) has passed.

Important: Make sure to prepare LUMRYZ at bedside.

1.) At your (or your child's) bedside, open the mixing cup by twisting the cap to the left (counter-clockwise) to remove it.

2.) Fill the mixing cup with water up to Fill Line A (top line) and set the mixing cup down on a flat surface.

3.) Open 1 packet:

Use scissors to cut open the packet along the Cutting Line, located on the back of the packet.

Fold the packet in half at the gray Tear Mark located on the back of the packet.

Tear the packet open with your hands.

4.) Pour the entire content from the packet into the water-filled mixing cup.

Make sure there is no powder left in the packet.

5.) Close the mixing cup by twisting the cap to the right (clockwise) until firmly closed.

6.) Mix the water and powder solution by shaking the closed mixing cup well for at least 60 seconds (1 minute).

7.) Make sure the solution is mixed thoroughly.

The mixed solution will appear slightly milky with some lumps.

The mixing cup cap is not child resistant. If the mixed solution is not drank immediately, then do not remove the cap, and keep out of reach of children.

8.) Open the mixing cup by twisting the cap to the left (counter-clockwise) and remove it.

9.) While sitting in bed drink (or have your child drink) the mixed solution within 30 minutes of mixing.

Make sure you (or your child) drink all the mixed solution in the mixing cup.

10.) Immediately refill the mixing cup with water up to Fill Line B (lower line) to mix in any medicine left in the mixing cup.

Do not open another packet of LUMRYZ. Take (or give) only 1 packet each day at bedtime.

11.) Close the mixing cup by twisting the cap to the right (clockwise) until firmly closed.

12.) Shake well again for 10 seconds.

13.) Open the mixing cup by twisting the cap to the left (counter-clockwise) and remove it.

14.) Drink (or have your child drink) the mixed solution immediately after mixing.

Make sure you (or your child) drink all the mixed solution in the mixing cup.

15.) Leave the empty mixing cup at your (or your child's) bedside and immediately lie down (or have your child lie down) to go to sleep.

Avoid getting out of your bed (or having your child get out of bed) after taking LUMRYZ.

16.) The next day, place the empty LUMRYZ packet in the trash.

If any LUMRYZ remains in the packet, rinse it down the sink before (prior to) throwing away (disposal).

17.) Empty any unused LUMRYZ down the sink drain the next day.

Clean the mixing cup by rinsing it with water and letting it dry before each use.

After you (or your child) finish all of the packets in the LUMRYZ carton

After you have (or your child has) finished your (or your child's) last packet in the carton, throw away the rinsed mixing cup in the trash.

If you have additional questions about LUMRYZ, talk with your doctor.

You can also contact:

Avadel CNS Pharmaceuticals, LLC

Chesterfield, MO 63005 USA

For more information on LUMRYZ,

visit www.lumryz.com or call

888-8AVADEL (888-828-2335).

© Avadel 2025. All rights reserved. AVADEL, the AVADEL logo, LUMRYZ, and the LUMRYZ logo are trademarks of an Avadel company.

This Instructions for Use has been approved by the U.S. Food and Drug Administration.

Revised: 11/2025

PACKAGE LABEL

PRINCIPAL DISPLAY PANEL - NDC: 13551-001-01 - 4.5 g Packet Label

PACKAGE LABEL

PRINCIPAL DISPLAY PANEL - NDC: 13551-001-07 - 4.5 g 7-count Carton Label

PACKAGE LABEL

PRINCIPAL DISPLAY PANEL - NDC: 13551-001-30 - 4.5 g 30-count Carton Label

PACKAGE LABEL

PRINCIPAL DISPLAY PANEL - NDC: 13551-002-01 - 6 g Packet Label

PACKAGE LABEL

PRINCIPAL DISPLAY PANEL - NDC: 13551-002-07 - 6 g 7-count Carton Label

PACKAGE LABEL

PRINCIPAL DISPLAY PANEL - NDC: 13551-002-30 - 6 g 30-count Carton Label

PACKAGE LABEL

PRINCIPAL DISPLAY PANEL - NDC: 13551-003-01 - 7.5 g Packet Label

PACKAGE LABEL

PRINCIPAL DISPLAY PANEL - NDC: 13551-003-07 - 7.5 g 7-count Carton Label

PACKAGE LABEL

PRINCIPAL DISPLAY PANEL - NDC: 13551-003-30 - 7.5 g 30-count Carton Label

PACKAGE LABEL

PRINCIPAL DISPLAY PANEL - NDC: 13551-004-01 - 9 g Packet Label

PACKAGE LABEL

PRINCIPAL DISPLAY PANEL - NDC: 13551-004-07 - 9 g 7-count Carton Label

PACKAGE LABEL

PRINCIPAL DISPLAY PANEL - NDC: 13551-004-30 - 9 g 30-count Carton Label